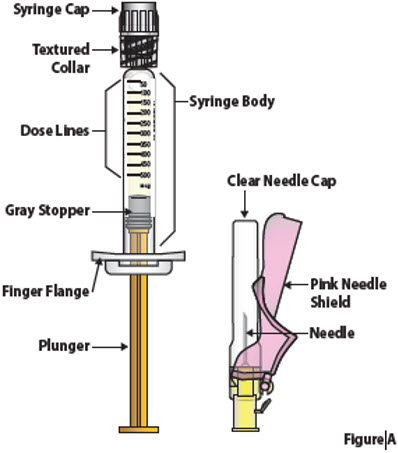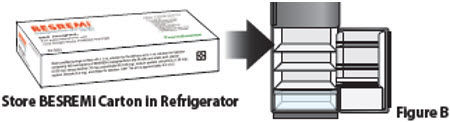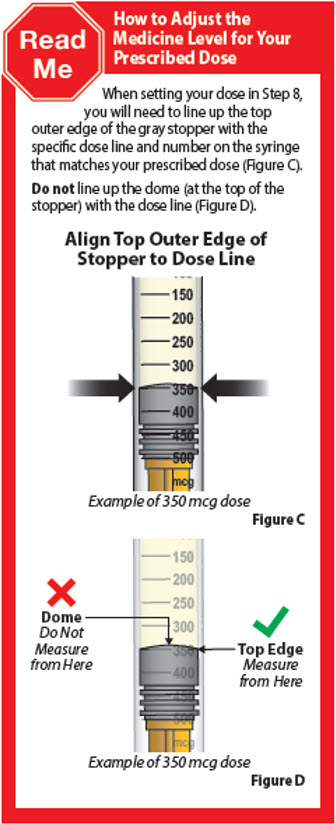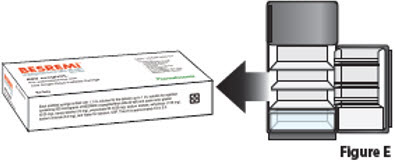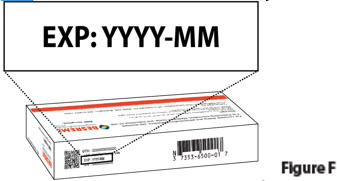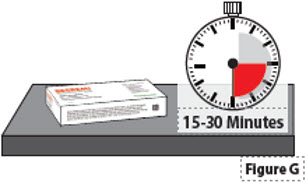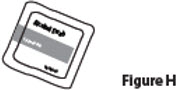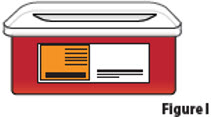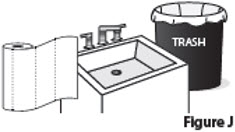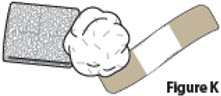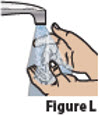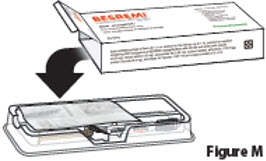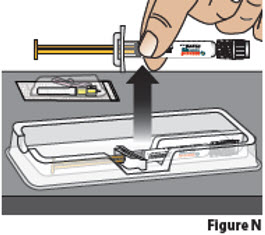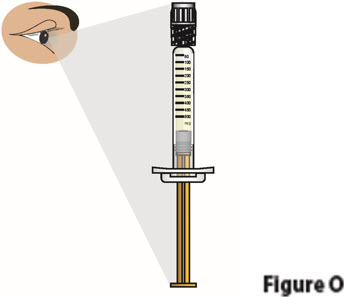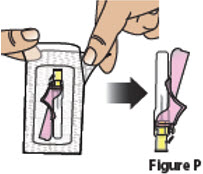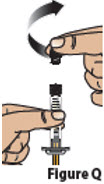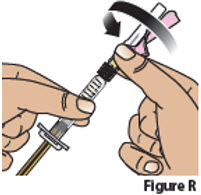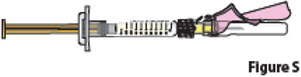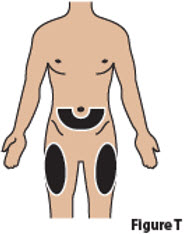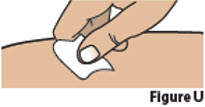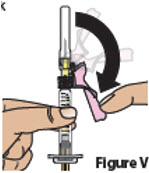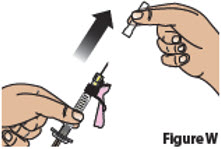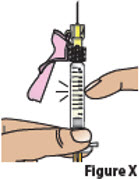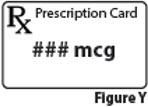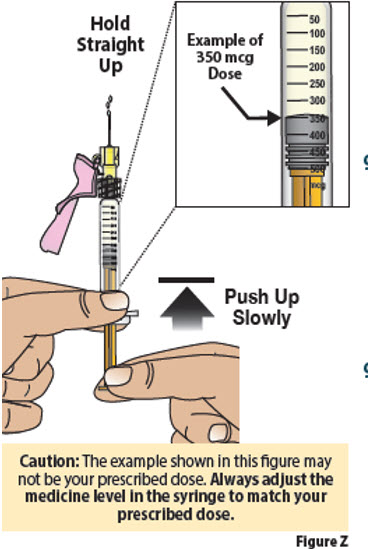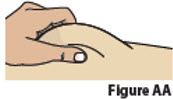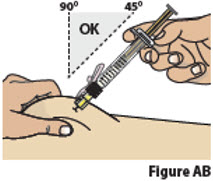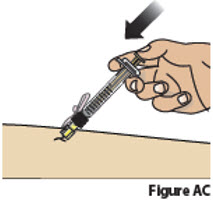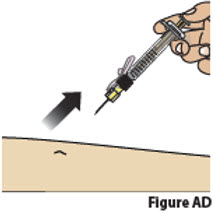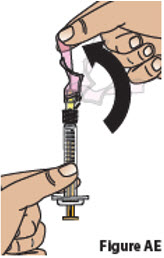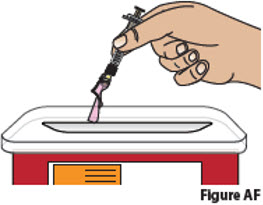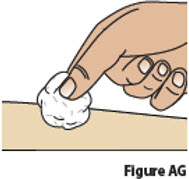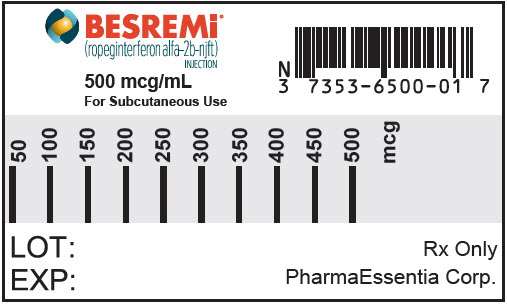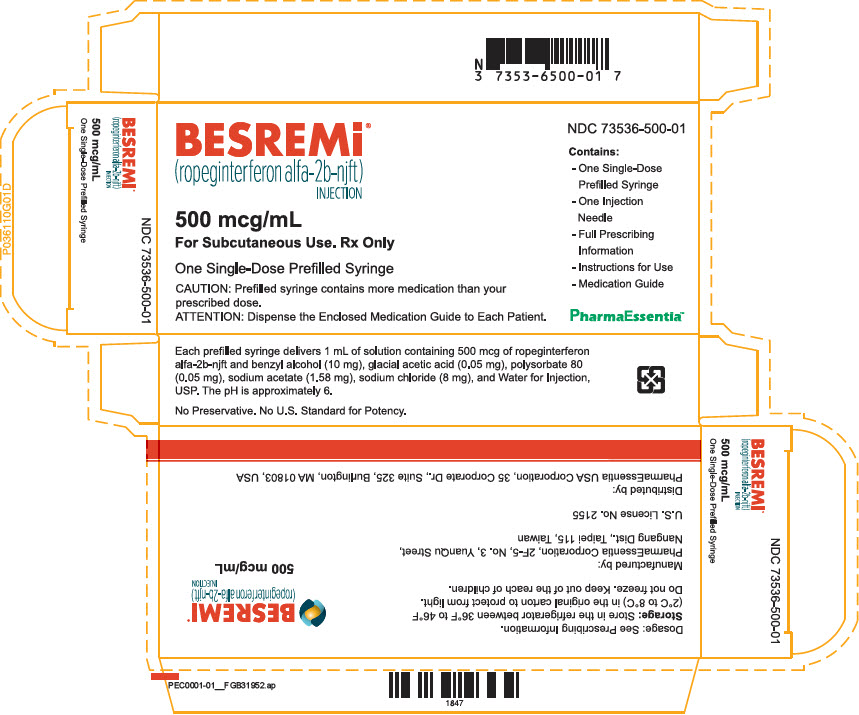 DRUG LABEL: BESREMi
NDC: 73536-500 | Form: INJECTION
Manufacturer: PharmaEssentia USA
Category: prescription | Type: HUMAN PRESCRIPTION DRUG LABEL
Date: 20260116

ACTIVE INGREDIENTS: ROPEGINTERFERON ALFA-2B 500 ug/1 mL
INACTIVE INGREDIENTS: BENZYL ALCOHOL 10 mg/1 mL; ACETIC ACID; POLYSORBATE 80; SODIUM ACETATE; SODIUM CHLORIDE; WATER

HIGHLIGHTS OF PRESCRIBING INFORMATION

These highlights do not include all the information needed to use BESREMi safely and effectively. See full prescribing information for BESREMi. BESREMI (ropeginterferon alfa-2b-njft) injection, for subcutaneous use Initial U.S. Approval: 2021

These highlights do not include all the information needed to use BESREMi safely and effectively. See full prescribing information for BESREMi. BESREMi (ropeginterferon alfa-2b-njft) injection, for subcutaneous use Initial U.S. Approval: 2021 WARNING: RISK OF SERIOUS DISORDERS

WARNING: RISK OF SERIOUS DISORDERS

See full prescribing information for complete boxed warning.

Risk of Serious Disorders: Interferon alfa products may cause or aggravate fatal or life-threatening neuropsychiatric, autoimmune, ischemic, and infectious disorders. Monitor closely and withdraw therapy with persistently severe or worsening signs or symptoms of the above disorders.

1 INDICATIONS AND USAGE

BESREMi is an interferon alfa-2b indicated for the treatment of adults with polycythemia vera (1)

2 DOSAGE AND ADMINISTRATION

- Recommended starting dose: 100 mcg by subcutaneous injection every 2 weeks (50 mcg if receiving hydroxyurea).
- Increase the dose by 50 mcg every 2 weeks (up to a maximum of 500 mcg) until hematological parameters are stabilized (2.1)
- Interrupt or discontinue dosing if certain adverse reactions occur (2.3, 5)

3 DOSAGE FORMS AND STRENGTHS

- Injection: 500 mcg/mL solution in a single-dose prefilled syringe (3)

4 CONTRAINDICATIONS

- Existence of, or history of severe psychiatric disorders, particularly severe depression, suicidal ideation or suicide attempt (4)
- Hypersensitivity to interferon or to any component of BESREMi (4)
- Hepatic impairment (Child-Pugh B or C) (4)
- History or presence of active serious or untreated autoimmune disease (4)
- Immunosuppressed transplant recipients (4)

5 WARNINGS AND PRECAUTIONS

Patients exhibiting the following events should be closely monitored and may require dose reduction or discontinuation of therapy:

- Depression and Suicide: Monitor closely for symptoms and need for treatment. (5.1)
- Endocrine Toxicity: Discontinue if endocrine disorders occur that cannot be medically managed. (5.2)
- Cardiovascular Toxicity: Avoid use in patients with severe, acute or unstable cardiovascular disease. Monitor patients with history of cardiovascular disorders more frequently. (5.3)
- Decreased Peripheral Blood Counts: Perform blood counts at baseline, every 2 weeks during titration, and at least every 3-6 months during maintenance treatment. (5.4)
- Hypersensitivity Reactions: Stop treatment and immediately manage reaction. (5.5)
- Pancreatitis: Consider discontinuation if confirmed pancreatitis (5.6)
- Colitis: Discontinue if signs or symptoms of colitis (5.7)
- Pulmonary Toxicity: Discontinue if pulmonary infiltrates or pulmonary function impairment (5.8)
- Ophthalmologic Toxicity: Advise patients to have eye examinations before and during treatment. Evaluate eye symptoms promptly and discontinue if new or worsening eye disorders. (5.9)
- Hyperlipidemia: Monitor serum triglycerides before BESREMi treatment and intermittently during therapy and manage when elevated. (5.10)
- Hepatotoxicity: Monitor liver enzymes and hepatic function at baseline and during treatment. Reduce dose or discontinue depending on severity. (5.11)
- Renal Toxicity: Monitor serum creatinine at baseline and during therapy. Discontinue if severe renal impairment develops. (5.12)
- Dental and Periodontal Toxicity: Advise patients on good oral hygiene and to have regular dental examinations. (5.13)
- Dermatologic Toxicity: Consider discontinuing if clinically significant dermatologic toxicity. (5.14)
- Driving and Operating Machinery: Advise patients to avoid driving or using machinery if they experience dizziness, somnolence, or hallucination. (5.15)

6 ADVERSE REACTIONS

The most common adverse reactions reported in > 40% of patients were influenza-like illness, arthralgia, fatigue, pruritus, nasopharyngitis, and musculoskeletal pain (6).

To report SUSPECTED ADVERSE REACTIONS, contact PharmaEssentia at 1-800-999-2449 or FDA at 1-800-FDA-1088 or www.fda.gov/medwatch.

7 DRUG INTERACTIONS

- Monitor patients taking CYP450 substrates with a narrow therapeutic index for adverse reactions to inform the need for dose adjustment of the concomitant drug (7.1)
- Avoid use with myelosuppressive agents and monitor patients receiving the combination for effects of excessive myelosuppression (7.2)
- Avoid use with narcotics, hypnotics or sedatives. Monitor patients receiving the combination for excessive central nervous system toxicity (7.3)

8 USE IN SPECIFIC POPULATIONS

- Pregnancy: Can cause fetal harm. Advise females of reproductive potential of the potential risk to a fetus and to use effective contraception. (8.1, 8.3)
- Lactation: Breastfeeding not recommended. (8.2)
- Renal Impairment: Avoid use in patients with eGFR <30 mL/min. (8.6)

FULL PRESCRIBING INFORMATION

These highlights do not include all the information needed to use BESREMi safely and effectively. See full prescribing information for BESREMi. BESREMi (ropeginterferon alfa-2b-njft) injection, for subcutaneous use Initial U.S. Approval: 2021 WARNING: RISK OF SERIOUS DISORDERS

Risk of Serious Disorders: Interferon alfa products may cause or aggravate fatal or life-threatening neuropsychiatric, autoimmune, ischemic, and infectious disorders. Patients should be monitored closely with periodic clinical and laboratory evaluations. Therapy should be withdrawn in patients with persistently severe or worsening signs or symptoms of these conditions. In many, but not all cases, these disorders resolve after stopping therapy [ see Warnings and Precautions (5.1, 5,2, 5.3, 5.4) and Adverse Reactions (6.1)].

1 INDICATIONS AND USAGE

BESREMi is indicated for the treatment of adults with polycythemia vera.

2 DOSAGE AND ADMINISTRATION

2.1 Pre-Treatment Testing
Obtain a pregnancy test in females of reproductive potential prior to initiating treatment with BESREMi [see Use in Specific Populations (8.3)].

2.2 Recommended Dosage
Patients Not Already on Hydroxyurea:

- The recommended BESREMi starting dosage for patients not on hydroxyurea is 100 mcg by subcutaneous injection every two weeks.
- Increase the dose by 50 mcg every two weeks (up to a maximum of 500 mcg), until the hematological parameters are stabilized (hematocrit less than 45%, platelets less than 400 x 109/L, and leukocytes less than 10 x 109/L).

Patients Transitioning from Hydroxyurea:

- When transitioning to BESREMi from hydroxyurea, start BESREMi at 50 mcg by subcutaneous injection every two weeks in combination with hydroxyurea.
- Gradually taper off the hydroxyurea by reducing the total biweekly dose by 20-40% every two weeks during Weeks 3-12.
- Increase the dose of BESREMi by 50 mcg every two weeks (up to a maximum of 500 mcg), until the hematological parameters are stabilized (hematocrit less than 45%, platelets less than 400 x 109/L, and leukocytes less than 10 x 109/L).
- Discontinue hydroxyurea by Week 13.

Maintain the two-week dosing interval of BESREMi at which hematological stability is achieved for at least 1 year. After achievement of hematological stability for at least 1 year on a stable dose of BESREMi, the dosing interval may be expanded to every 4 weeks.

Monitor patients closely especially during the titration phase. Perform complete blood counts (CBC) regularly, every 2 weeks during the titration phase and every 3-6 months during the maintenance phase (after the patient’s optimal dose is established). Monitor CBC more frequently if clinically indicated. Phlebotomy as rescue treatment to normalize blood hyperviscosity may be necessary during the titration phase [see Clinical Pharmacology (12.2)].
2.3 Dose Modifications
Monitor CBC every 2 weeks during the titration phase and dose modification phase. Phlebotomy as rescue treatment to normalize blood hyperviscosity may be necessary [see Clinical Pharmacology (12.2)].

If dose interruption occurs, resume dosing at previously attained levels. If drug-related toxicities arise, reduce the dose to the next lower level or interrupt in accordance with the table below (Table 1). If there is insufficient efficacy at the decreased dose following dose modification, a dose increase attempt to the next higher dose level should be considered after recovery to grade 1 toxicity.

Table 1 Dose Modifications for BESREMi Adverse Reactions

Adverse Reactiona | Severity | Dosage Modification
Liver enzyme elevation with; concomitant bilirubin elevation, or; other evidence of hepatic; decompensation | Any increase above baseline | Interrupt treatment until recovery, restart at dose 50 mcg lower than; the interrupted dose. If the interrupted dose is 50 mcg, refrain from treatment until recovery.; Consider permanent discontinuation if toxicity persists after four dose- modifications.
Liver enzyme elevation | >5 x the upper limit of normal (ULN) but ≤20 x ULN | Decrease dose by 50 mcg; if toxicity does not improve, continue decreasing at biweekly intervals until alanine aminotransferase (ALT) and aspartate aminotransferase (AST) recover < 3 x ULN if baseline was normal; 3 x baseline if baseline was abnormal, and gamma-glutamyltransferase (GGT) recovers to < 2.5 x ULN if baseline was normal; 2.5 x baseline if baseline was abnormal.; If the interrupted dose is 50 mcg, refrain from treatment until recovery.
 | >20 x ULN | Interrupt treatment until ALT and AST recover to < 3 x ULN if baseline was normal; 1.5 x baseline if baseline was abnormal, and gamma-glutamyltransferase (GGT) recovers to < 2.5 x ULN if baseline was normal; 2 x baseline if baseline was abnormal. Consider permanent discontinuation if toxicity persists after four dose-modifications.
Cytopenia | Anemia: Hemoglobin (Hgb) < 8 g/dL; Thrombocytopenia: platelet count < 50,000/mm3 but ≥25,000/mm3; Leukopenia: white blood cell count (WBC) <2000/mm3 but; ≥1,000/mm3 | Decrease dose by 50 mcg; if toxicity does not improve, continue decreasing at biweekly intervals until recovery of Hgb >10.0 g/dL, platelets >75,000/mm3, and WBC >3,000/mm3; If the interrupted dose is 50 mcg, refrain from treatment until recovery.
 | Anemia: Hemoglobin levels are life threatening, or urgent intervention needed; Thrombocytopenia: platelet count <25,000/mm3; Leukopenia: WBC <1000/mm3 | Interrupt treatment until recovery of Hgb >10.0 g/dL, platelets >75,000/mm3, and WBC >3,000/mm3.; Consider permanent discontinuation if toxicity persists after four dose-modifications.
Depression | Mild, without suicidal ideation; Moderate, without suicidal ideation; Severe, or any severity with suicidal ideation | Consider psychiatric consultation if persistent (>8 weeks).; Consider dose reduction and psychiatric consultation.; Discontinue therapy, recommend psychiatric consultation.

aNational Cancer Institute Common Terminology Criteria for Adverse Events (CTCAE), version 3.0

2.4 Preparation and Administration
Read the INSTRUCTIONS FOR USE before administering the single-dose BESREMi prefilled syringe. BESREMi is for subcutaneous injection only and may be administered by either a healthcare professional, a patient or a caregiver. Before a decision is made to allow BESREMi to be administered by a patient or caregiver, ensure that the patient is an appropriate candidate for self-administration or administration by a caregiver. Proper training on storage, preparation and administration technique should be provided. If a patient or caregiver is not an appropriate candidate for any reason, then BESREMi should be administered by a healthcare professional.

Before each injection, remove the carton that contains the BESREMi prefilled syringe from the refrigerator. Keep the prefilled syringe in the carton and lay it flat on a clean work surface for 15-30 minutes to allow the prefilled syringe to reach room temperature [59 ˚F to 77 ˚F (15 ˚C to 25 ˚C)].

Before injection, visually inspect BESREMi in the prefilled syringe for particulate matter and discoloration before administration (do not use if the solution in the syringe is cloudy, discolored, contains particulate matter or if the syringe shows any sign of damage).

Syringe Preparation

- Remove the prefilled syringe cap by unscrewing it counterclockwise.
- Attach the covered needle to the prefilled syringe by firmly pushing it onto the collar of the syringe and then screwing (turn clockwise) it on until it feels securely attached.
- Choose one of the following injection sites: Lower stomach (abdomen) area, at least 2 inches away from the belly button, or top of thighs. Rotate (change) the injection site for each injection. Do not inject into skin that is irritated, red, bruised, infected, or scarred; clean the chosen injection site with an alcohol swab and let air dry.
- Uncap needle and move air bubbles to top. Pull the pink needle shield back and hold the syringe from the syringe body. Remove the clear needle cap by pulling it straight off. Throw away the needle cap into the trash. Hold the prefilled syringe with the needle pointing up. Tap on the body of the prefilled syringe to move any air bubbles to the top.

Set Injection Dose

- Depending on the prescribed dose, the amount of dose in the syringe may need to be adjusted by discarding some of the medication.
- Hold the prefilled syringe at eye level with the needle pointing straight up over a paper towel, sink, or trash can. Check that you can see the dose lines and number markings on the prefilled syringe.
- Pinch the end of the plunger and slowly push up to remove liquid medicine until the top edge of the gray stopper lines up with the marking for the prescribed dose.

Inject BESREMi

- Pinch the chosen injection site. While pinching the skin, insert needle at a 45- to 90-degree angle into the pinched skin, then release the pinched skin.
- Inject BESREMi by slowly pressing on the plunger all the way until it stops. After all the liquid medicine is injected, remove the needle from the skin.

Dispose of Used Syringe

- Carefully push the pink needle shield over the needle until it snaps into place and covers the needle. Do not recap the needle using the needle cap; only use the pink needle shield to cover the needle.
- Throw away the used prefilled syringe with the needle still attached, into an FDA-cleared sharps disposal container.

2.1 Pre-Treatment Testing

Pregnancy testing is recommended prior to BESREMi treatment in females of reproductive potential [see Use in Specific Populations (8.3)] .

2.2 Recommended Dosage

Patients Not Already on Hydroxyurea:

- The recommended BESREMi starting dosage for patients not on hydroxyurea is 100 mcg by subcutaneous injection every two weeks.
- Increase the dose by 50 mcg every two weeks (up to a maximum of 500 mcg), until the hematological parameters are stabilized (hematocrit less than 45%, platelets less than 400 × 10^9/L, and leukocytes less than 10 × 10^9/L).

Patients Transitioning from Hydroxyurea:

- When transitioning to BESREMi from hydroxyurea, start BESREMi at 50 mcg by subcutaneous injection every two weeks in combination with hydroxyurea.
- Gradually taper off the hydroxyurea by reducing the total biweekly dose by 20-40% every two weeks during Weeks 3-12.
- Increase the dose of BESREMi by 50 mcg every two weeks (up to a maximum of 500 mcg), until the hematological parameters are stabilized (hematocrit less than 45%, platelets less than 400 × 10^9/L, and leukocytes less than 10 × 10^9/L).
- Discontinue hydroxyurea by Week 13.

Maintain the two week dosing interval of BESREMi at which hematological stability is achieved for at least 1 year. After achievement of hematological stability for at least 1 year on a stable dose of BESREMi, the dosing interval may be expanded to every 4 weeks.

Monitor patients closely especially during the titration phase. Perform complete blood counts (CBC) regularly, every 2 weeks during the titration phase and every 3-6 months during the maintenance phase (after the patient's optimal dose is established). Monitor CBC more frequently if clinically indicated. Phlebotomy as rescue treatment to normalize blood hyperviscosity may be necessary during the titration phase [see Clinical Pharmacology (12.2)] .

2.3 Dose Modifications

Monitor CBC every 2 weeks during the titration phase and dose modification phase. Phlebotomy as rescue treatment to normalize blood hyperviscosity may be necessary [see Clinical Pharmacology (12.2)] .

If dose interruption occurs, resume dosing at previously attained levels. If drug-related toxicities arise, reduce the dose to the next lower level or interrupt in accordance with the table below (Table 1). If there is insufficient efficacy at the decreased dose following dose modification, a dose increase attempt to the next higher dose level should be considered after recovery to grade 1 toxicity.

Table 1 Dose Modifications for BESREMi Adverse Reactions
Adverse Reaction [National Cancer Institute Common Terminology Criteria for Adverse Events (CTCAE), version 3.0] | Severity | Dosage Modification
Liver enzyme elevation with concomitant bilirubin elevation, or other evidence of hepatic decompensation | Any increase above baseline | Interrupt treatment until recovery, restart at dose 50 mcg lower than the interrupted dose. If the interrupted dose is 50 mcg, refrain from treatment until recovery. Consider permanent discontinuation if toxicity persists after four dose-modifications.
Liver enzyme elevation | >5 × the upper limit of normal (ULN) but ≤20 × ULN | Decrease dose by 50 mcg; if toxicity does not improve, continue decreasing at biweekly intervals until alanine aminotransferase (ALT) and aspartate aminotransferase (AST) recover < 3 × ULN if baseline was normal; 3 × baseline if baseline was abnormal, and gamma-glutamyltransferase (GGT) recovers to < 2.5 × ULN if baseline was normal; 2.5 × baseline if baseline was abnormal.
Liver enzyme elevation | >5 × the upper limit of normal (ULN) but ≤20 × ULN | If the interrupted dose is 50 mcg, refrain from treatment until recovery.
 | >20 × ULN | Interrupt treatment until ALT and AST recover to < 3 × ULN if baseline was normal; 1.5 × baseline if baseline was abnormal, and gamma-glutamyltransferase (GGT) recovers to < 2.5 × ULN if baseline was normal; 2 × baseline if baseline was abnormal. Consider permanent discontinuation if toxicity persists after four dose-modifications.
Cytopenia | Anemia: Hemoglobin (Hgb) < 8 g/dL | Decrease dose by 50 mcg; if toxicity does not improve, continue decreasing at biweekly intervals until recovery of Hgb >10.0 g/dL, platelets >75,000/mm^3, and WBC >3,000/mm^3
Cytopenia | Thrombocytopenia: platelet count < 50,000/mm^3 but ≥25,000/mm^3 | Decrease dose by 50 mcg; if toxicity does not improve, continue decreasing at biweekly intervals until recovery of Hgb >10.0 g/dL, platelets >75,000/mm^3, and WBC >3,000/mm^3
Cytopenia | Leukopenia: white blood cell count (WBC) <2000/mm^3 but ≥1,000/mm^3 | Decrease dose by 50 mcg; if toxicity does not improve, continue decreasing at biweekly intervals until recovery of Hgb >10.0 g/dL, platelets >75,000/mm^3, and WBC >3,000/mm^3
Cytopenia |  | If the interrupted dose is 50 mcg, refrain from treatment until recovery.
 | Anemia: Hemoglobin levels are life threatening, or urgent intervention needed | Interrupt treatment until recovery of Hgb >10.0 g/dL, platelets >75,000/mm^3, and WBC >3,000/mm^3.
 | Thrombocytopenia: platelet count <25,000/mm^3 | Consider permanent discontinuation if toxicity persists after four dose-modifications.
 | Leukopenia: WBC <1000/mm^3
Depression | Mild, without suicidal ideation | Consider psychiatric consultation if persistent (>8 weeks).
 | Moderate, without suicidal ideation | Consider dose reduction and psychiatric consultation.
 | Severe, or any severity with suicidal ideation | Discontinue therapy, recommend psychiatric consultation.

2.4 Preparation and Administration

Read the INSTRUCTIONS FOR USE before administering the single-dose BESREMi prefilled syringe. BESREMi is for subcutaneous injection only and may be administered by either a healthcare professional, a patient or a caregiver. Before a decision is made to allow BESREMi to be administered by a patient or caregiver, ensure that the patient is an appropriate candidate for self-administration or administration by a caregiver. Proper training on storage, preparation and administration technique should be provided. If a patient or caregiver is not an appropriate candidate for any reason, then BESREMi should be administered by a healthcare professional.

Before each injection, remove the carton that contains the BESREMi prefilled syringe from the refrigerator. Keep the prefilled syringe in the carton and lay it flat on a clean work surface for 15-30 minutes to allow the prefilled syringe to reach room temperature [59 ˚F to 77 ˚F (15 ˚C to 25 ˚C)].

Before injection, visually inspect BESREMi in the prefilled syringe for particulate matter and discoloration before administration (do not use if the solution in the syringe is cloudy, discolored, contains particulate matter or if the syringe shows any sign of damage).

Syringe Preparation

- Remove the prefilled syringe cap by unscrewing it counterclockwise.
- Attach the covered needle to the prefilled syringe by firmly pushing it onto the collar of the syringe and then screwing (turn clockwise) it on until it feels securely attached.
- Choose one of the following injection sites: Lower stomach (abdomen) area, at least 2 inches away from the belly button, or top of thighs. Rotate (change) the injection site for each injection. Do not inject into skin that is irritated, red, bruised, infected, or scarred; clean the chosen injection site with an alcohol swab and let air dry.
- Uncap needle and move air bubbles to top. Pull the pink needle shield back and hold the syringe from the syringe body. Remove the clear needle cap by pulling it straight off. Throw away the needle cap into the trash. Hold the prefilled syringe with the needle pointing up. Tap on the body of the prefilled syringe to move any air bubbles to the top.

Set Injection Dose

- Depending on the prescribed dose, the amount of dose in the syringe may need to be adjusted by discarding some of the medication.
- Hold the prefilled syringe at eye level with the needle pointing straight up over a paper towel, sink, or trash can. Check that you can see the dose lines and number markings on the prefilled syringe.
- Pinch the end of the plunger and slowly push up to remove liquid medicine until the top edge of the gray stopper lines up with the marking for the prescribed dose.

Inject BESREMi

- Pinch the chosen injection site. While pinching the skin, insert needle at a 45- to 90-degree angle into the pinched skin, then release the pinched skin.
- Inject BESREMi by slowly pressing on the plunger all the way until it stops. After all the liquid medicine is injected, remove the needle from the skin.

Dispose of Used Syringe

- Carefully push the pink needle shield over the needle until it snaps into place and covers the needle. Do not recap the needle using the needle cap; only use the pink needle shield to cover the needle.
- Throw away the used prefilled syringe with the needle still attached, into an FDA-cleared sharps disposal container.

3 DOSAGE FORMS AND STRENGTHS

Injection: 500 mcg/mL clear and colorless to slightly yellowish solution in a single-dose prefilled syringe.

4 CONTRAINDICATIONS

BESREMi is contraindicated in patients with:

- Existence of, or history of severe psychiatric disorders, particularly severe depression, suicidal ideation, or suicide attempt
- Hypersensitivity to interferons including interferon alfa-2b or any of the inactive ingredients of BESREMi
- Moderate (Child-Pugh B) or severe (Child-Pugh C) hepatic impairment
- History or presence of active serious or untreated autoimmune disease
- History of transplantation and receiving immunosuppressant agents.

5 WARNINGS AND PRECAUTIONS

5.1 Depression and Suicide

Life-threatening or fatal neuropsychiatric reactions have occurred in patients receiving interferon alfa products, including BESREMi. These reactions may occur in patients with and without previous psychiatric illness. Serious neuropsychiatric reactions have been observed in 3% of patients treated with BESREMi during the clinical development program. Among the 178 patients in the clinical development program of BESREMi, 17 cases of depression, depressive symptoms, depressed mood, and listlessness occurred. Of these seventeen cases, 3.4% of the patients recovered with temporary drug interruption and 2.8% stopped BESREMi treatment.

Other central nervous system effects, including suicidal ideation, attempted suicide, aggression, bipolar disorder, mania and confusion have been observed with other interferon alfa products. BESREMi is contraindicated in patients with a history of severe psychiatric disorders, particularly severe depression, suicidal ideation, or suicide attempt [see Contraindications (4)].

Closely monitor patients for any symptoms of psychiatric disorders and consider psychiatric consultation and treatment if such symptoms emerge. If psychiatric symptoms worsen, it is recommended to discontinue BESREMi therapy.

5.2 Endocrine Toxicity

Endocrine toxicity has occurred in patients receiving interferon alfa products, including BESREMi. These toxicities may include worsening hypothyroidism and hyperthyroidism. Autoimmune thyroiditis and hyperglycemia, including new onset type 1 diabetes, have been reported in patients receiving interferon alfa-2b products. Eight cases of hyperthyroidism (4.5%), seven cases of hypothyroidism (3.9%) and five cases (2.8%) of autoimmune thyroiditis/thyroiditis occurred in the development program of BESREMi.

Do not use BESREMi in patients with active serious or untreated endocrine disorders associated with autoimmune disease [ Contraindications (4)]. Evaluate thyroid function in patients who develop symptoms suggestive of thyroid disease during BESREMi therapy. Discontinue BESREMi in patients who develop endocrine disorders that cannot be adequately managed during treatment with BESREMi.

5.3 Cardiovascular Toxicity

Cardiovascular toxicity has occurred in patients receiving interferon alfa products, including BESREMi. Toxicities may include cardiomyopathy, myocardial infarction, atrial fibrillation and coronary artery ischemia [see Adverse Reactions (6.1)]. Patients with a history of cardiovascular disorders should be closely monitored for cardiovascular toxicity during BESREMi therapy. Avoid use of BESREMi in patients with severe or unstable cardiovascular disease, (e.g., uncontrolled hypertension, congestive heart failure (≥ NYHA class 2), serious cardiac arrhythmia, significant coronary artery stenosis, unstable angina) or recent stroke or myocardial infarction.

5.4 Decreased Peripheral Blood Counts

Decreased peripheral blood counts have occurred in patients receiving interferon alfa products, including BESREMi. These toxicities may include thrombocytopenia (increasing the risk of bleeding), anemia, and leukopenia (increasing the risk of infection). Thrombocytopenia of grade 3 (platelet counts <50,000 – 25,000/mm3) or greater occurred in 2% of BESREMi-treated patients. Anemia of grade 3 (Hgb < 8 g/dL) or greater occurred in 1% of BESREMi-treated patients. Leukopenia of grade 3 (WBC counts <2,000 – 1,000/mm3) or greater occurred in 2% of BESREMi-treated patients. Infection occurred in 48% of BESREMi treated patients, while serious infections occurred in 8% of BESREMi treated patients. Monitor complete blood counts at baseline, during titration and every 3-6 months during the maintenance phase. Monitor patients for signs and symptoms of infection or bleeding.

5.5 Hypersensitivity Reactions

Hypersensitivity reactions have occurred in patients receiving interferon alfa products, including BESREMi. BESREMi is contraindicated in patients with hypersensitivity reactions to interferon products or any of the inactive ingredients in BESREMi [see Contraindications (4)]. Toxicities may include serious, acute hypersensitivity reactions (e.g., urticaria, angioedema, bronchoconstriction, anaphylaxis). If such reactions occur, discontinue BESREMi and institute appropriate medical therapy immediately. Transient rashes may not necessitate interruption of treatment.

5.6 Pancreatitis

Pancreatitis has occurred in patients receiving interferon alfa products, including BESREMi. Pancreatitis was reported in 2.2% of patients receiving BESREMi. Symptoms may include nausea, vomiting, upper abdominal pain, bloating, and fever. Patients may experience elevated lipase, amylase, white blood cell count, or altered renal/hepatic function. Interrupt BESREMi treatment in patients with possible pancreatitis and evaluate promptly. Consider discontinuation of BESREMi in patients with confirmed pancreatitis.

5.7 Colitis

Fatal and serious ulcerative or hemorrhagic/ischemic colitis have occurred in patients receiving interferon alfa products, some cases occurring as early as 12 weeks after start of treatment. Symptoms may include abdominal pain, bloody diarrhea, and fever. Discontinue BESREMi in patients who develop these signs or symptoms. Colitis may resolve within 1 to 3 weeks of stopping treatment.

5.8 Pulmonary Toxicity

Pulmonary toxicity has occurred in patients receiving interferon alfa products, including BESREMi. Pulmonary toxicity may manifest as dyspnea, pulmonary infiltrates, pneumonia, bronchiolitis obliterans, interstitial pneumonitis, pulmonary hypertension, and sarcoidosis. Some events have resulted in respiratory failure or death. Discontinue BESREMi in patients who develop pulmonary infiltrates or pulmonary function impairment.

5.9 Ophthalmologic Toxicity

Ophthalmologic toxicity has occurred in patients receiving interferon alfa products, including BESREMi. These toxicities may include severe eye disorders such as retinopathy, retinal hemorrhage, retinal exudates, retinal detachment and retinal artery or vein occlusion which may result in blindness. During BESREMi therapy, 23% of patients were identified with an eye disorder. Eyes disorders ≥5% included cataract (6%) and dry eye (5%). Advise patients to have eye examinations before and during BESREMi therapy, specifically in those patients with a retinopathy-associated disease such as diabetes mellitus or hypertension. Evaluate eye symptoms promptly. Discontinue BESREMi in patients who develop new or worsening eye disorders.

5.10 Hyperlipidemia

Hyperlipidemia has occurred in patients treated with interferon alfa products, including BESREMi. Hyperlipidemia, hypertriglyceridemia, or dyslipidemia occurred in 3% of patients receiving BESREMi. Elevated triglycerides may result in pancreatitis [see Warnings and Precautions (5.6)]. Monitor serum triglycerides before BESREMi treatment and intermittently during therapy and manage when elevated. Consider discontinuation of BESREMi in patients with persistently, markedly elevated triglycerides.

5.11 Hepatotoxicity

Hepatotoxicity has occurred in patients receiving interferon alfa products, including BESREMi. These toxicities may include increases in serum ALT, AST, GGT and bilirubin. BESREMi is contraindicated in patients with moderate (Child-Pugh B) or severe (Child-Pugh C) hepatic impairment [see Contraindications (4)].

Increases in serum ALT ≥3 times the upper limit of normal (ULN), AST ≥3 times the ULN, GGT ≥3 times the ULN, and bilirubin >2 times the ULN have been observed in patients treated with BESREMi.

In the clinical development program of BESREMi, 36 patients (20%) experienced liver enzyme elevations, 33 of whom had elevations of 1.25-5x ULN. Patients were able to resume BESREMi upon resolution of liver enzyme elevations. Liver enzyme elevations have also been reported in patients after long-term BESREMi therapy.

Monitor liver enzymes and hepatic function at baseline and during BESREMi treatment. Reduce BESREMi dosage by 50 mcg for increased AST/ALT/GGT then monitor AST/ALT/GGT weekly until the values return to baseline or grade 1 (ALT and AST < 3 x ULN if baseline was normal; 1.5 - 3 x baseline if baseline was abnormal, and GGT < 2.5 x ULN if baseline was normal; 2 - 2.5 x baseline if baseline was abnormal) [see Dosage and Administration (2.3)]. If toxicity does not improve, continue decreasing the BESREMi dose at biweekly intervals until recovery to grade 1. Hold if AST/ALT/GGT > 20 x ULN and consider permanent discontinuation if increased liver enzyme levels persist after four dose-reductions. Discontinue BESREMi in patients who develop evidence of hepatic decompensation (characterized by jaundice, ascites, hepatic encephalopathy, hepatorenal syndrome or variceal hemorrhage) during treatment [see Use in Specific Populations (8.7)].

5.12 Renal Toxicity

Renal toxicity has occurred in patients receiving interferon alfa products, including BESREMi. During BESREMi therapy, <1% of patients were reported to develop renal impairment and <1% of patients were reported to have toxic nephropathy. Monitor serum creatinine at baseline and during therapy. Avoid use of BESREMi in patients with eGFR <30 mL/min. Discontinue BESREMi if severe renal impairment develops during treatment [see Use in Specific Populations (8.6)].

5.13 Dental and Periodontal Toxicity

Dental and periodontal toxicities may occur in patients receiving interferon alfa products, including BESREMi. These toxicities may include dental and periodontal disorders, which may lead to loss of teeth. In addition, dry mouth could have a damaging effect on teeth and oral mucous membranes during long-term treatment with BESREMi. Patients should have good oral hygiene and regular dental examinations.

5.14 Dermatologic Toxicity

Dermatologic toxicity has occurred in patients receiving interferon alfa products, including BESREMi. These toxicities have included skin rash, pruritus, alopecia, erythema, psoriasis, xeroderma, dermatitis acneiform, hyperkeratosis, and hyperhidrosis. Consider discontinuation of BESREMi if clinically significant dermatologic toxicity occurs.

5.15 Driving and Operating Machinery

BESREMi may impact the ability to drive and use machinery. Patients should not drive or use heavy machinery until they know how BESREMi affects their abilities. Patients who experience dizziness, somnolence or hallucination during BESREMi therapy should avoid driving or using machinery.

5.16 Embryo-Fetal Toxicity

Based on the mechanism of action, BESREMi can cause fetal harm when administered to a pregnant woman [see Use in Specific Populations (8.1) and Clinical Pharmacology (12.1)]. Obtain a pregnancy test in females of reproductive potential prior to initiating treatment with BESREMi. Advise females of reproductive potential to use an effective method of contraception during treatment with BESREMi and for at least 8 weeks after the final dose [see Dosage and Administration (2.1) and Use in Specific Populations (8.1, 8.3)].

5.1 Depression and Suicide

Life-threatening or fatal neuropsychiatric reactions have occurred in patients receiving interferon alfa products, including BESREMi. These reactions may occur in patients with and without previous psychiatric illness. Serious neuropsychiatric reactions have been observed in 3% of patients treated with BESREMi during the clinical development program. Among the 178 patients in the clinical development program of BESREMi, 17 cases of depression, depressive symptoms, depressed mood, and listlessness occurred. Of these seventeen cases, 3.4% of the patients recovered with temporary drug interruption and 2.8% stopped BESREMi treatment.

Other central nervous system effects, including suicidal ideation, attempted suicide, aggression, bipolar disorder, mania and confusion have been observed with other interferon alfa products. BESREMi is contraindicated in patients with a history of severe psychiatric disorders, particularly severe depression, suicidal ideation, or suicide attempt [see Contraindications (4)] .

Closely monitor patients for any symptoms of psychiatric disorders and consider psychiatric consultation and treatment if such symptoms emerge. If psychiatric symptoms worsen, it is recommended to discontinue BESREMi therapy.

5.2 Endocrine Toxicity

Endocrine toxicity has occurred in patients receiving interferon alfa products, including BESREMi. These toxicities may include worsening hypothyroidism and hyperthyroidism. Autoimmune thyroiditis and hyperglycemia, including new onset type 1 diabetes, have been reported in patients receiving interferon alfa-2b products. Eight cases of hyperthyroidism (4.5%), seven cases of hypothyroidism (3.9%) and five cases (2.8%) of autoimmune thyroiditis/thyroiditis occurred in the development program of BESREMi.

Do not use BESREMi in patients with active serious or untreated endocrine disorders associated with autoimmune disease [Contraindications (4)]. Evaluate thyroid function in patients who develop symptoms suggestive of thyroid disease during BESREMi therapy. Discontinue BESREMi in patients who develop endocrine disorders that cannot be adequately managed during treatment with BESREMi.

5.3 Cardiovascular Toxicity

Cardiovascular toxicity has occurred in patients receiving interferon alfa products, including BESREMi. Toxicities may include cardiomyopathy, myocardial infarction, atrial fibrillation and coronary artery ischemia [see Adverse Reactions (6.1)] . Patients with a history of cardiovascular disorders should be closely monitored for cardiovascular toxicity during BESREMi therapy. Avoid use of BESREMi in patients with severe or unstable cardiovascular disease, (e.g., uncontrolled hypertension, congestive heart failure (≥ NYHA class 2), serious cardiac arrhythmia, significant coronary artery stenosis, unstable angina) or recent stroke or myocardial infarction.

5.4 Decreased Peripheral Blood Counts

Decreased peripheral blood counts have occurred in patients receiving interferon alfa products, including BESREMi. These toxicities may include thrombocytopenia (increasing the risk of bleeding), anemia, and leukopenia (increasing the risk of infection). Thrombocytopenia of grade 3 (platelet counts <50,000 – 25,000/mm^3) or greater occurred in 2% of BESREMi-treated patients. Anemia of grade 3 (Hgb < 8 g/dL) or greater occurred in 1% of BESREMi-treated patients. Leukopenia of grade 3 (WBC counts <2,000 – 1,000/mm^3) or greater occurred in 2% of BESREMi-treated patients. Infection occurred in 48% of BESREMi treated patients, while serious infections occurred in 8% of BESREMi treated patients. Monitor complete blood counts at baseline, during titration and every 3-6 months during the maintenance phase. Monitor patients for signs and symptoms of infection or bleeding.

5.5 Hypersensitivity Reactions

Hypersensitivity reactions have occurred in patients receiving interferon alfa products, including BESREMi. BESREMi is contraindicated in patients with hypersensitivity reactions to interferon products or any of the inactive ingredients in BESREMi [see Contraindications (4)] . Toxicities may include serious, acute hypersensitivity reactions (e.g., urticaria, angioedema, bronchoconstriction, anaphylaxis). If such reactions occur, discontinue BESREMi and institute appropriate medical therapy immediately. Transient rashes may not necessitate interruption of treatment.

5.6 Pancreatitis

Pancreatitis has occurred in patients receiving interferon alfa products, including BESREMi. Pancreatitis was reported in 2.2% of patients receiving BESREMi. Symptoms may include nausea, vomiting, upper abdominal pain, bloating, and fever. Patients may experience elevated lipase, amylase, white blood cell count, or altered renal/hepatic function. Interrupt BESREMi treatment in patients with possible pancreatitis and evaluate promptly. Consider discontinuation of BESREMi in patients with confirmed pancreatitis.

5.7 Colitis

Fatal and serious ulcerative or hemorrhagic/ischemic colitis have occurred in patients receiving interferon alfa products, some cases occurring as early as 12 weeks after start of treatment. Symptoms may include abdominal pain, bloody diarrhea, and fever. Discontinue BESREMi in patients who develop these signs or symptoms. Colitis may resolve within 1 to 3 weeks of stopping treatment.

5.8 Pulmonary Toxicity

Pulmonary toxicity has occurred in patients receiving interferon alfa products, including BESREMi. Pulmonary toxicity may manifest as dyspnea, pulmonary infiltrates, pneumonia, bronchiolitis obliterans, interstitial pneumonitis, pulmonary hypertension, and sarcoidosis. Some events have resulted in respiratory failure or death. Discontinue BESREMi in patients who develop pulmonary infiltrates or pulmonary function impairment.

5.9 Ophthalmologic Toxicity

Ophthalmologic toxicity has occurred in patients receiving interferon alfa products, including BESREMi. These toxicities may include severe eye disorders such as retinopathy, retinal hemorrhage, retinal exudates, retinal detachment and retinal artery or vein occlusion which may result in blindness. During BESREMi therapy, 23% of patients were identified with an eye disorder. Eyes disorders ≥5% included cataract (6%) and dry eye (5%). Advise patients to have eye examinations before and during BESREMi therapy, specifically in those patients with a retinopathy-associated disease such as diabetes mellitus or hypertension. Evaluate eye symptoms promptly. Discontinue BESREMi in patients who develop new or worsening eye disorders.

5.10 Hyperlipidemia

Hyperlipidemia has occurred in patients treated with interferon alfa products, including BESREMi. Hyperlipidemia, hypertriglyceridemia, or dyslipidemia occurred in 3% of patients receiving BESREMi. Elevated triglycerides may result in pancreatitis [see Warnings and Precautions (5.6)] . Monitor serum triglycerides before BESREMi treatment and intermittently during therapy and manage when elevated. Consider discontinuation of BESREMi in patients with persistently, markedly elevated triglycerides.

5.11 Hepatotoxicity

Hepatotoxicity has occurred in patients receiving interferon alfa products, including BESREMi. These toxicities may include increases in serum ALT, AST, GGT and bilirubin. BESREMi is contraindicated in patients with moderate (Child-Pugh B) or severe (Child-Pugh C) hepatic impairment [see Contraindications (4)] .

Increases in serum ALT ≥3 times the upper limit of normal (ULN), AST ≥3 times the ULN, GGT ≥3 times the ULN, and bilirubin >2 times the ULN have been observed in patients treated with BESREMi.

In the clinical development program of BESREMi, 36 patients (20%) experienced liver enzyme elevations, 33 of whom had elevations of 1.25-5× ULN. Patients were able to resume BESREMi upon resolution of liver enzyme elevations. Liver enzyme elevations have also been reported in patients after long-term BESREMi therapy.

Monitor liver enzymes and hepatic function at baseline and during BESREMi treatment. Reduce BESREMi dosage by 50 mcg for increased AST/ALT/GGT then monitor AST/ALT/GGT weekly until the values return to baseline or grade 1 (ALT and AST < 3 × ULN if baseline was normal; 1.5 - 3 × baseline if baseline was abnormal, and GGT < 2.5 × ULN if baseline was normal; 2 - 2.5 × baseline if baseline was abnormal) [see Dosage and Administration (2.3)]. If toxicity does not improve, continue decreasing the BESREMi dose at biweekly intervals until recovery to grade 1. Hold if AST/ALT/GGT > 20 × ULN and consider permanent discontinuation if increased liver enzyme levels persist after four dose-reductions. Discontinue BESREMi in patients who develop evidence of hepatic decompensation (characterized by jaundice, ascites, hepatic encephalopathy, hepatorenal syndrome or variceal hemorrhage) during treatment [see Use in Specific Populations (8.7)] .

5.12 Renal Toxicity

Renal toxicity has occurred in patients receiving interferon alfa products, including BESREMi. During BESREMi therapy, <1% of patients were reported to develop renal impairment and <1% of patients were reported to have toxic nephropathy. Monitor serum creatinine at baseline and during therapy. Avoid use of BESREMi in patients with eGFR <30 mL/min. Discontinue BESREMi if severe renal impairment develops during treatment [see Use in Specific Populations (8.6)] .

5.13 Dental and Periodontal Toxicity

Dental and periodontal toxicities may occur in patients receiving interferon alfa products, including BESREMi. These toxicities may include dental and periodontal disorders, which may lead to loss of teeth. In addition, dry mouth could have a damaging effect on teeth and oral mucous membranes during long-term treatment with BESREMi. Patients should have good oral hygiene and regular dental examinations.

5.14 Dermatologic Toxicity

Dermatologic toxicity has occurred in patients receiving interferon alfa products, including BESREMi. These toxicities have included skin rash, pruritus, alopecia, erythema, psoriasis, xeroderma, dermatitis acneiform, hyperkeratosis, and hyperhidrosis. Consider discontinuation of BESREMi if clinically significant dermatologic toxicity occurs.

5.15 Driving and Operating Machinery

BESREMi may impact the ability to drive and use machinery. Patients should not drive or use heavy machinery until they know how BESREMi affects their abilities. Patients who experience dizziness, somnolence or hallucination during BESREMi therapy should avoid driving or using machinery.

5.16 Embryo-Fetal Toxicity

Based on the mechanism of action, BESREMi can cause fetal harm when administered to a pregnant woman [see Clinical Pharmacology (12.1) and Use in Specific Populations (8.1)] . Pregnancy testing is recommended in females of reproductive potential prior to treatment with BESREMi. Advise females of reproductive potential to use an effective method of contraception during treatment with BESREMi and for at least 8 weeks after the final dose [see Dosage and Administration (2.1) and Use in Specific Populations (8.1, 8.3)] .

6 ADVERSE REACTIONS

The following clinically significant adverse reactions are described elsewhere in the labeling.

- Depression and Suicide [see Warnings and Precautions (5.1)]
- Endocrine Toxicity [see Warnings and Precautions (5.2)]
- Cardiovascular Toxicity [see Warnings and Precautions (5.3)]
- Decreased Peripheral Blood Counts [see Warnings and Precautions (5.4)]
- Hypersensitivity Reactions [see Warnings and Precautions (5.5)]
- Pancreatitis [see Warnings and Precautions (5.6)]
- Colitis [see Warnings and Precautions (5.7)]
- Pulmonary Toxicity [see Warnings and Precautions (5.8)]
- Ophthalmologic Toxicity [see Warnings and Precautions (5.9)]
- Hyperlipidemia [see Warnings and Precautions (5.10)]
- Hepatotoxicity [see Warnings and Precautions (5.11)]
- Renal Toxicity [see Warnings and Precautions (5.12)]
- Dental and Periodontal Toxicity [see Warnings and Precautions (5.13)]
- Dermatologic Toxicity [see Warnings and Precautions (5.14)]
- Driving and Operating Machinery [see Warnings and Precautions (5.15)]

6.1 Clinical Trials Experience
Because clinical trials are conducted under widely varying conditions, adverse reaction rates observed in the clinical trials of a drug cannot be directly compared to rates in the clinical trials of another drug and may not reflect the rates observed in practice.
The pooled safety population described in the Warnings and Precautions section reflects exposure to BESREMi as monotherapy for the treatment of polycythemia vera dosed every two to four weeks in 178 patients in two open-label trials [PEGINVERA, PROUD/CONTINUATION PV]. The mean age at baseline was 58.6 years (range 30-85 years), 88 (49.4%) women, 90 (50.6%) men, 177 (99%) Caucasian and 1 (1%) Asian. Among 178 patients who received BESREMi, 80% were exposed for 12 months or longer. The mean dose of BESREMi was 334 mcg SD ± 121 during the treatment period. In this pooled safety population, the most common adverse reactions greater than 10%, were liver enzyme elevations (20%), leukopenia (20%), thrombocytopenia (19%), arthralgia (13%), fatigue (12%), myalgia (11%), and influenza-like illness (11%).
The safety findings described below reflect exposure to BESREMi as monotherapy for the treatment of polycythemia vera in 51 patients in the PEGINVERA study [see Clinical Studies (14)]. Among the 51 patients receiving BESREMi, 71% were exposed for 12 months or longer, 63% were exposed for three years or longer, and 53% were exposed for greater than five years.

Serious adverse reactions were reported in 16% of patients in the PEGINVERA study. The most common serious adverse reactions observed during the study (> 4%) included urinary tract infection (8%), transient ischemic attack (6%) and depression (4%).

Adverse reactions requiring permanent discontinuation in >2% of patients who received BESREMi included depression (8%) arthralgia (4%), fatigue (4%), and general physical health deterioration (4%) In the PEGINVERA study, patients were not pre-screened for depression or anxiety disorders.

The most common adverse reactions reported in ≥10% of patients in the PEGINVERA study are listed in Table 2.

Table 2 Adverse Reactions in > 10% of Subjects with Polycythemia Vera in the PEGINVERA Study Over 7.5 Years.

Adverse Reactions* | BESREMi; N=51; %
Influenza-like illnessa | 59
Arthralgia | 47
Fatigueb | 47
Pruritis | 45
Nasopharyngitisc | 43
Musculoskeletal paind | 41
Headachee | 39
Diarrhea | 33
Hyperhidrosisf | 29
Nausea | 28
Upper respiratory tract infectiong | 27
Local administration site reactions | 26
Dizziness | 22
Abdominal painh | 20
Depression | 20
Sleep disorderi | 20
Leukopenia | 18
Decreased appetite | 18
Alopecia | 16
Edemaj | 16
Hypertensionk | 16
Muscle spasms | 16
Neutropenia | 16
Rashl | 16
Transaminase elevationsm | 16
Urinary tract infection | 16
Thrombocytopenia | 12
Vertigo | 12

*Adverse Reactions defined as all treatment emergent adverse events

Grouped Term Definitions

a Includes pyrexia, chills, and influenza-like illness.

b Includes asthenia, malaise, and fatigue.

c Includes pharyngitis and nasopharyngitis.

d Includes musculoskeletal pain, back pain, pain in extremity, bone pain, flank pain, and spinal pain.

e Includes headache, migraine, and head pain.
f Includes night sweats and hyperhidrosis.
g Includes upper respiratory tract infection, rhinitis, bronchitis, and respiratory tract infection.
h Includes abdominal pain upper, abdominal pain lower, and abdominal pain.
i Includes insomnia, sleep disorder, and abnormal dreams.
j Includes peripheral edema and generalized edema.
k Includes hypertension and hypertensive crisis.
l Includes rash, maculopapular rash, and pruritic rash.
m Includes transaminase increase, hepatic enzyme increase, GGT increase, AST increase, and ALT increase.

Cardiovascular System: Atrial fibrillation

6.1 Clinical Trials Experience

The following clinically significant adverse reactions are described elsewhere in the labeling.

- Depression and Suicide [see Warnings and Precautions (5.1)]
- Endocrine Toxicity [see Warnings and Precautions (5.2)]
- Cardiovascular Toxicity [see Warnings and Precautions (5.3)]
- Decreased Peripheral Blood Counts [see Warnings and Precautions (5.4)]
- Hypersensitivity Reactions [see Warnings and Precautions (5.5)]
- Pancreatitis [see Warnings and Precautions (5.6)]
- Colitis [see Warnings and Precautions (5.7)]
- Pulmonary Toxicity [see Warnings and Precautions (5.8)]
- Ophthalmologic Toxicity [see Warnings and Precautions (5.9)]
- Hyperlipidemia [see Warnings and Precautions (5.10)]
- Hepatotoxicity [see Warnings and Precautions (5.11)]
- Renal Toxicity [see Warnings and Precautions (5.12)]
- Dental and Periodontal Toxicity [see Warnings and Precautions (5.13)]
- Dermatologic Toxicity [see Warnings and Precautions (5.14)]
- Driving and Operating Machinery [see Warnings and Precautions (5.15)]
- Embryo-Fetal Toxicity [see Warnings and Precautions (5.16)]

Because clinical trials are conducted under widely varying conditions, adverse reaction rates observed in the clinical trials of a drug cannot be directly compared to rates in the clinical trials of another drug and may not reflect the rates observed in practice.

The pooled safety population described in the Warnings and Precautions section reflects exposure to BESREMi as monotherapy for the treatment of polycythemia vera dosed every two to four weeks in 178 patients in two open-label trials [ PEGINVERA, PROUD/CONTINUATION PV]. The mean age at baseline was 58.6 years (range 30-85 years), 88 (49.4%) women, 90 (50.6%) men, 177 (99%) Caucasian and 1 (1%) Asian. Among 178 patients who received BESREMi, 80% were exposed for 12 months or longer. The mean dose of BESREMi was 334 mcg SD ± 121 during the treatment period. In this pooled safety population, the most common adverse reactions greater than 10%, were liver enzyme elevations (20%), leukopenia (20%), thrombocytopenia (19%), arthralgia (13%), fatigue (12%), myalgia (11%), and influenza-like illness (11%).

The safety findings described below reflect exposure to BESREMi as monotherapy for the treatment of polycythemia vera in 51 patients in the PEGINVERA study [see Clinical Studies (14)] . Among the 51 patients receiving BESREMi, 71% were exposed for 12 months or longer, 63% were exposed for three years or longer, and 53% were exposed for greater than five years.

Serious adverse reactions were reported in 16% of patients in the PEGINVERA study. The most common serious adverse reactions observed during the study (≥ 4%) included urinary tract infection (8%), transient ischemic attack (6%) and depression (4%).

Adverse reactions requiring permanent discontinuation in >2% of patients who received BESREMi included depression (8%), arthralgia (4%), fatigue (4%), and general physical health deterioration (4%) In the PEGINVERA study, patients were not pre-screened for depression or anxiety disorders.

The most common adverse reactions reported in ≥10% of patients in the PEGINVERA study are listed in Table 2.

Table 2 Adverse Reactions in > 10% of Subjects with Polycythemia Vera in the PEGINVERA Study Over 7.5 Years.
Adverse Reactions [Adverse Reactions defined as all treatment emergent adverse events] | BESREMi N=51 %
Influenza-like illness [Includes pyrexia, chills, and influenza-like illness.] | 59
Arthralgia | 47
Fatigue [Includes asthenia, malaise, and fatigue.] | 47
Pruritis | 45
Nasopharyngitis [Includes pharyngitis and nasopharyngitis.] | 43
Musculoskeletal pain [Includes musculoskeletal pain, back pain, pain in extremity, bone pain, flank pain, and spinal pain.] | 41
Headache [Includes headache, migraine, and head pain.] | 39
Diarrhea | 33
Hyperhidrosis [Includes night sweats and hyperhidrosis.] | 29
Nausea | 28
Upper respiratory tract infection [Includes upper respiratory tract infection, rhinitis, bronchitis, and respiratory tract infection.] | 27
Local administration site reactions | 26
Dizziness | 22
Abdominal pain [Includes abdominal pain upper, abdominal pain lower, and abdominal pain.] | 20
Depression | 20
Sleep disorder [Includes insomnia, sleep disorder, and abnormal dreams.] | 20
Leukopenia | 18
Decreased appetite | 18
Alopecia | 16
Edema [Includes peripheral edema and generalized edema.] | 16
Hypertension [Includes hypertension and hypertensive crisis.] | 16
Muscle spasms | 16
Neutropenia | 16
Rash [Includes rash, maculopapular rash, and pruritic rash.] | 16
Transaminase elevations [Includes transaminase increase, hepatic enzyme increase, GGT increase, AST increase, and ALT increase.] | 16
Urinary tract infection | 16
Thrombocytopenia | 12
Vertigo | 12
Grouped Term Definitions

Clinically relevant adverse reactions in < 10% of patients include:

Cardiovascular System: Atrial fibrillation

6.2 Immunogenicity

As with all therapeutic proteins, there is potential for immunogenicity. The detection of antibody formation is highly dependent on the sensitivity and specificity of the assay. Additionally, the observed incidence of antibody (including neutralizing antibody) positivity in an assay may be influenced by several factors, including assay methodology, sample handling, timing of sample collection, concomitant medications, and underlying disease. For these reasons, comparison of the incidence of antibodies in the studies described below with the incidence of antibodies in other studies or to other interferon alfa-2b products may be misleading.

The incidence of binding antibodies to ropeginterferon alfa-2b-njft was 1.4% (2/146) and they were observed as early as 8 weeks post-dosing. Among the patients who tested positive for binding antibodies, none developed neutralizing antibodies.

7 DRUG INTERACTIONS

7.1 Drugs Metabolized by Cytochrome P450

Certain proinflammatory cytokines, including interferons, can suppress CYP450 enzymes resulting in increased exposures of some CYP substrates [see Clinical Pharmacology (12.3)]. Therefore, patients on BESREMi who are receiving concomitant drugs that are CYP450 substrates with a narrow therapeutic index should be monitored to inform the need for dosage modification for these concomitant drugs.

7.2 Myelosuppressive Agents

Concomitant use of BESREMi and myelosuppressive agents can produce additive myelosuppression. Avoid use and monitor patients receiving the combination for effects of excessive myelosuppression [see Warnings and Precautions (5.4)].

7.3 Narcotics, Hypnotics or Sedatives

Concomitant use of BESREMi and narcotics, hypnotics or sedatives can produce additive neuropsychiatric side effects. Avoid use and monitor patients receiving the combination for effects of excessive CNS toxicity [see Warnings and Precautions (5.1)].

7.1 Drugs Metabolized by Cytochrome P450

Certain proinflammatory cytokines, including interferons, can suppress CYP450 enzymes resulting in increased exposures of some CYP substrates [see Clinical Pharmacology (12.3)] . Therefore, patients on BESREMi who are receiving concomitant drugs that are CYP450 substrates with a narrow therapeutic index should be monitored to inform the need for dosage modification for these concomitant drugs.

7.2 Myelosuppressive Agents

Concomitant use of BESREMi and myelosuppressive agents can produce additive myelosuppression. Avoid use and monitor patients receiving the combination for effects of excessive myelosuppression [see Warnings and Precautions (5.4)] .

7.3 Narcotics, Hypnotics or Sedatives

Concomitant use of BESREMi and narcotics, hypnotics or sedatives can produce additive neuropsychiatric side effects. Avoid use and monitor patients receiving the combination for effects of excessive CNS toxicity [see Warnings and Precautions (5.1)] .

8 USE IN SPECIFIC POPULATIONS

8.1 Pregnancy
Risk Summary
Available human data with BESREMi use in pregnant women are insufficient to identify a drug-associated risk of
major birth defects, miscarriage or adverse maternal or fetal outcomes. An abortifacient effect was reported in
cynomolgus monkeys receiving ropeginterferon alfa-2b (see Data). Based on mechanism of action and the role of
interferon alfa in pregnancy and fetal development, BESREMi may cause fetal harm and should be assumed to have
abortifacient potential when administered to a pregnant woman. There are adverse effects on maternal and fetal
outcomes associated with polycythemia vera in pregnancy (see Clinical Considerations). Advise pregnant women of
the potential risk to a fetus.

The estimated background risk of major birth defects and miscarriage for the indicated population is unknown. All
pregnancies have a background risk of birth defect, loss, or other adverse outcomes. In the U.S. general population,
the estimated background risk of major birth defects and miscarriage is 2-4% and 15-20%, respectively.

Data

Animal Data
In an embryo-fetal development study, pregnant cynomolgus monkeys received subcutaneous injection of
ropeginterferon alfa-2b twice weekly during the period of organogenesis (Gestation Days 20-48). Maternal toxicity,
characterized by a significant decline in food consumption and transient body weight loss, occurred at all dose levels
and ropeginterferon alfa-2b was abortifacient and caused embryonic death at exposures 275-times (Cmax) and 64-times
(AUC) the human exposure at the maximum recommended human dose of 500 μg. There were no effects on fetal

developmental parameters or abnormalities in the surviving fetuses (GD 100) where the ropeginterferon alfa-2b
exposures achieved in pregnant cynomolgus monkeys during the first trimester were 961-times (Cmax) and 224-times
(AUC) the human exposure at the maximum recommended human dose of 500 μg.

Clinical Considerations
Disease-Associated Maternal and/or Embryo-Fetal Risk

Untreated polycythemia vera during pregnancy is associated with adverse maternal outcomes such as thrombosis and
hemorrhage. Adverse pregnancy outcomes associated with polycythemia vera include increased risk for miscarriage.

8.2 Lactation
There are no data on the presence of BESREMi in human or animal milk, the effects on the breastfed child, or the
effects on milk production. Because of the potential for serious adverse reactions in breastfed children from BESREMi,
advise women not to breastfeed during treatment and for 8 weeks after the final dose.

8.3 Females and Males of Reproductive Potential
BESREMi may cause embryo-fetal harm when administered to a pregnant woman [see Use in Specific Populations (8.1)].
Pregnancy Testing
Pregnancy testing prior to BESREMi treatment is recommended for females of reproductive potential.

Contraception
Females
Advise female patients of reproductive potential to use effective contraception during treatment with BESREMi and
for at least 8 weeks after the final dose.

Infertility
Females
Based on its mechanism of action, BESREMi can cause disruption of the menstrual cycle [see Clinical Pharmacology (12.1)]. No animal fertility studies have been conducted with BESREMi.

8.4 Pediatric Use
Safety and effectiveness in pediatric patients have not been established.

8.5 Geriatric Use
There were 17 patients 65 years of age and older in the clinical study in polycythemia vera [see Clinical Studies (14)].
Of the total number of BESREMi-treated patients in this study, 17 (33%) were 65 years of age and older, while 5
(9.8%) were 75 years of age and older. Clinical studies of BESREMi did not include sufficient numbers of subjects
aged 65 years and over to determine whether they respond differently from younger subjects. Other reported clinical
experience has not identified differences in responses between the elderly and younger patients.

8.6 Renal Impairment
No dose adjustment is necessary in patients with estimated glomerular filtration rate (eGFR) ≥30 mL/min [see Clinical Pharmacology (12.3)]. Avoid use of BESREMi in patients with eGFR <30 mL/min [see Warnings and Precautions (5.12)].

8.7 Hepatic Impairment
BESREMi is contraindicated in patients with hepatic impairment (Child-Pugh B or C) [see Contraindications (4)].
Increased liver enzyme levels have been observed in patients treated with BESREMi. When the increase in liver
enzyme levels is progressive and persistent, reduce the dose of BESREMi. If the increase in liver enzymes is
progressive and clinically significant despite dose-reduction, or if there is evidence of hepatic impairment (Child-Pugh
B or C), discontinue BESREMi [see Dosage and Administration (2.2) and Warnings and Precautions (5.11)].

8.1 Pregnancy

Risk Summary

Available human data with BESREMi use in pregnant women are insufficient to identify a drug-associated risk of major birth defects, miscarriage or adverse maternal or fetal outcomes. Animal studies assessing reproductive toxicity of BESREMi have not been conducted. Based on mechanism of action and the role of interferon alfa in pregnancy and fetal development, BESREMi may cause fetal harm and should be assumed to have abortifacient potential when administered to a pregnant woman. There are adverse effects on maternal and fetal outcomes associated with polycythemia vera in pregnancy (see Clinical Considerations) . Advise pregnant women of the potential risk to a fetus.

The estimated background risk of major birth defects and miscarriage for the indicated population is unknown. All pregnancies have a background risk of birth defect, loss, or other adverse outcomes. In the U.S. general population, the estimated background risk of major birth defects and miscarriage is 2-4% and 15-20%, respectively.

Clinical Considerations

Disease-Associated Maternal and/or Embryo-Fetal Risk

Untreated polycythemia vera during pregnancy is associated with adverse maternal outcomes such as thrombosis and hemorrhage. Adverse pregnancy outcomes associated with polycythemia vera include increased risk for miscarriage.

8.2 Lactation

There are no data on the presence of BESREMi in human or animal milk, the effects on the breastfed child, or the effects on milk production. Because of the potential for serious adverse reactions in breastfed children from BESREMi, advise women not to breastfeed during treatment and for 8 weeks after the final dose.

8.3 Females and Males of Reproductive Potential

BESREMi may cause embryo-fetal harm when administered to a pregnant woman [see Use in Specific Populations (8.1)] .

Pregnancy Testing

Pregnancy testing prior to BESREMi treatment is recommended for females of reproductive potential.

Contraception

Females

Advise female patients of reproductive potential to use effective contraception during treatment with BESREMi and for at least 8 weeks after the final dose.

Infertility

Females

Based on its mechanism of action, BESREMi can cause disruption of the menstrual cycle [see Clinical Pharmacology (12.1)] . No animal fertility studies have been conducted with BESREMi.

8.4 Pediatric Use

Safety and effectiveness in pediatric patients have not been established.

8.5 Geriatric Use

Clinical studies of BESREMi did not include sufficient numbers of subjects aged 65 years and over to determine whether they respond differently from younger subjects. Other reported clinical experience has not identified differences in responses between the elderly and younger patients. In general, dose selection for an elderly patient should be cautious, usually starting at the low end of the dosing range, reflecting the greater frequency of decreased hepatic, renal, or cardiac function and of concomitant disease or other therapy.

8.6 Renal Impairment

No dose adjustment is necessary in patients with estimated glomerular filtration rate (eGFR) ≥30 mL/min [see Clinical Pharmacology (12.3)]. Avoid use of BESREMi in patients with eGFR <30 mL/min [see Warnings and Precautions (5.12)].

8.7 Hepatic Impairment

BESREMi is contraindicated in patients with hepatic impairment (Child-Pugh B or C) [see Contraindications (4)] .

Increased liver enzyme levels have been observed in patients treated with BESREMi. When the increase in liver enzyme levels is progressive and persistent, reduce the dose of BESREMi. If the increase in liver enzymes is progressive and clinically significant despite dose-reduction, or if there is evidence of hepatic impairment (Child-Pugh B or C), discontinue BESREMi [see Dosage and Administration (2.2) and Warnings and Precautions (5.11)] .

10 OVERDOSAGE

Overdosage of BESREMi may result in influenza-like symptoms or other adverse reactions. There is no antidote to BESREMi overdosage. In case of an overdose, frequently monitor signs and symptoms for adverse reactions.

11 DESCRIPTION

Ropeginterferon alfa-2b-njft, an interferon alfa-2b, is an N-terminal monopegylated covalent conjugate of proline interferon alfa-2b, produced in Escherichia coli cells by recombinant DNA technology, with a methoxy polyethylene glycol (mPEG) moiety. Ropeginterferon alfa-2b-njft has an approximate molecular weight of 60 kDa and the approximate molecular weight of the PEG portion of the molecule is 40 kDa.

BESREMi (ropeginterferon alfa-2b-njft) injection is a sterile, preservative-free, clear and colorless to slightly yellowish solution for subcutaneous use supplied in a single dose prefilled syringe.

Each prefilled syringe delivers 1 mL of solution containing 500 mcg of ropeginterferon alfa-2b-njft and benzyl alcohol (10 mg), glacial acetic acid (0.05 mg), polysorbate 80 (0.05 mg), sodium acetate (1.58 mg), sodium chloride (8 mg), and Water for Injection, USP. The pH is approximately 6.

12 CLINICAL PHARMACOLOGY

12.1 Mechanism of Action

Interferon alfa belongs to the class of type I interferons, which exhibit their cellular effects in polycythemia vera in the bone marrow by binding to a transmembrane receptor termed interferon alfa receptor (IFNAR). Binding to IFNAR initiates a downstream signaling cascade through the activation of kinases, in particular Janus kinase 1 (JAK1) and tyrosine kinase 2 (TYK2) and activator of transcription (STAT) proteins. Nuclear translocation of STAT proteins controls distinct gene-expression programs and exhibits various cellular effects The actions involved in the therapeutic effects of interferon alfa in polycythemia vera are not fully elucidated.

12.2 Pharmacodynamics

The efficacy of ropeginterferon alfa-2b-njft is dependent on the stabilization of hematological parameters (hematocrit

<45%, platelets <400 × 109/L and leukocytes <10 × 109/L). Pharmacokinetic-pharmacodynamic analyses have demonstrated that the reduction in the individual hematological parameters is dependent on ropeginterferon alfa-2b- njft concentrations. Complete hematological response (CHR, defined as a patient achieving hematocrit <45% without phlebotomy [at least 2 months since last phlebotomy], platelets ≤400 x 109/L and leukocytes ≤10 x 109/L) increased with increasing ropeginterferon alfa-2b-njft concentration over time. Based on the exposure-response (E-R) analyses using data from the PEGINVERA study, the predicted probability of CHR (95% Prediction Intervals) was 22% (11% – 34%) before treatment, 50% (38% – 62%) at week 20 (end of titration), 64% (47% – 78%) at week 52, and 70% (55% – 88%) at week 104. The E-R analyses show that the maximum probability of CHR is reached after 2 years of continuous treatment.

12.3 Pharmacokinetics

In patients with polycythemia vera, the estimated steady state Cmax, Cmin and area under the curve (AUC) after a two- week dosing interval of BESREMi over a dose range of 100 mcg to 500 mcg ranged from 4.4 – 31 ng/mL, 1.4 – 12 ng/mL, and 1011 – 7809 ng×h/mL, respectively. The estimated steady state Cmax occurs between 2 to 5 days.

Absorption

The estimated geometric mean (CV%) of the absorption rate constant of BESREMi is 0.12 day-1 (27%) in patients with polycythemia vera.

Distribution

The estimated geometric mean (CV%) of apparent volume of distribution of BESREMi is 4.8 L (21%) in patients with polycythemia vera.

Elimination

BESREMi undergoes receptor independent degradation/excretion and receptor binding and subsequent degradation of the drug-receptor complex. The half-life and clearance of BESREMi is approximately 7 days and 1.7-2.5 L/h in patients with polycythemia vera over a dose range of 100 mcg to 500 mcg, respectively.

Specific Populations

No clinically significant differences in the pharmacokinetics of BESREMi were observed based on age, sex, body surface area, and JAK2V617F mutation.

Drug Interactions

Clinical Studies

No clinical studies evaluating the drug interaction potential of BESREMi have been conducted.

In Vitro Studies

In vitro studies indicate that BESREMi exhibited time-dependent inhibitory potential on CYP2A6. BESREMi did not inhibit CYP1A2, CYP2B6, CYP2C8, CYP2C9, CYP2C19, CYP2D6, CYP2E1, and CYP3A4 in human liver

microsomes. BESREMi is not expected to induce CYP enzymes. However, interferon may influence CYP450 through modulating transcription factors and altering protein expression and/or structure. As this mechanism requires more time to exert effect, it cannot be evaluated by in vitro assays.

12.6 Immunogenicity

The observed incidence of anti-drug antibodies is highly dependent on the sensitivity and specificity of the assay. Differences in assay methods preclude meaningful comparisons of the incidence of anti-drug antibodies in the studies described below with the incidence of anti-drug antibodies in other studies, including those of ropeginterferon alfa-2b-njft or of other ropeginterferon alfa-2b products. From a total of 146 subjects evaluated in PEGINVERA, PROUD-PV and CONTINUATION-PV studies who have been followed for as long as 362 week with sampling every 8 weeks or 3 months during the first year post administration then every 3 or 6 months until the end of the study, the incidence of anti-drug antibodies was 1.4% (2/146) and were observed as early as 8 weeks post-dosing. No neutralizing antibodies were detected.

12.1 Mechanism of Action

Interferon alfa belongs to the class of type I interferons, which exhibit their cellular effects in polycythemia vera in the bone marrow by binding to a transmembrane receptor termed interferon alfa receptor (IFNAR). Binding to IFNAR initiates a downstream signaling cascade through the activation of kinases, in particular Janus kinase 1 (JAK1) and tyrosine kinase 2 (TYK2) and activator of transcription (STAT) proteins. Nuclear translocation of STAT proteins controls distinct gene-expression programs and exhibits various cellular effects. The actions involved in the therapeutic effects of interferon alfa in polycythemia vera are not fully elucidated.

12.2 Pharmacodynamics

The efficacy of ropeginterferon alfa-2b-njft is dependent on the stabilization of hematological parameters (hematocrit <45%, platelets <400 × 10^9/L and leukocytes <10 × 10^9/L). Pharmacokinetic-pharmacodynamic analyses have demonstrated that the reduction in the individual hematological parameters is dependent on ropeginterferon alfa-2b-njft concentrations. Complete hematological response (CHR, defined as a patient achieving hematocrit <45% without phlebotomy [at least 2 months since last phlebotomy], platelets ≤400 × 10^9/L and leukocytes ≤10 × 10^9/L) increased with increasing ropeginterferon alfa-2b-njft concentration over time. Based on the exposure-response (E-R) analyses using data from the PEGINVERA study, the predicted probability of CHR (95% Prediction Intervals) was 22% (11% – 34%) before treatment, 50% (38% – 62%) at week 20 (end of titration), 64% (47% – 78%) at week 52, and 70% (55% – 88%) at week 104. The E-R analyses show that the maximum probability of CHR is reached after 2 years of continuous treatment.

12.3 Pharmacokinetics

In patients with polycythemia vera, the estimated steady state Cmax, Cmin and area under the curve (AUC) after a two-week dosing interval of BESREMi over a dose range of 100 mcg to 500 mcg ranged from 4.4 – 31 ng/mL, 1.4 – 12 ng/mL, and 1011 – 7809 ng×h/mL, respectively. The estimated steady state Cmax occurs between 2 to 5 days.

Absorption

The estimated geometric mean (CV%) of the absorption rate constant of BESREMi is 0.12 day^-1 (27%) in patients with polycythemia vera.

Distribution

The estimated geometric mean (CV%) of apparent volume of distribution of BESREMi is 4.8 L (21%) in patients with polycythemia vera.

Elimination

BESREMi undergoes receptor independent degradation/excretion and receptor binding and subsequent degradation of the drug-receptor complex. The half-life and clearance of BESREMi is approximately 7 days and 1.7-2.5 L/h in patients with polycythemia vera over a dose range of 100 mcg to 500 mcg, respectively.

Specific Populations

No clinically significant differences in the pharmacokinetics of BESREMi were observed based on age, sex, body surface area, and JAK2V617F mutation.

Drug Interactions

Clinical Studies

No clinical studies evaluating the drug interaction potential of BESREMi have been conducted.

In Vitro Studies

In vitro studies indicate that BESREMi exhibited time-dependent inhibitory potential on CYP2A6. BESREMi did not inhibit CYP1A2, CYP2B6, CYP2C8, CYP2C9, CYP2C19, CYP2D6, CYP2E1, and CYP3A4 in human liver microsomes. BESREMi is not expected to induce CYP enzymes. However, interferon may influence CYP450 through modulating transcription factors and altering protein expression and/or structure. As this mechanism requires more time to exert effect, it cannot be evaluated by in vitro assays.

13 NONCLINICAL TOXICOLOGY

13.1 Carcinogenesis, Mutagenesis, Impairment of Fertility

Ropeginterferon alfa-2b-njft has not been tested for its carcinogenic potential. Neither ropeginterferon alfa-2b-njft nor its components, interferon or methoxypolyethylene glycol, caused damage to DNA when tested in the standard battery of mutagenesis assays. Ropeginterferon alfa-2b-njft effects on fertility have not been assessed [see Use in Specific Populations (8.1, 8.2, 8.3)].

13.1 Carcinogenesis, Mutagenesis, Impairment of Fertility

Ropeginterferon alfa-2b-njft has not been tested for its carcinogenic potential. Neither ropeginterferon alfa-2b-njft nor its components, interferon or methoxypolyethylene glycol, caused damage to DNA when tested in the standard battery of mutagenesis assays. Ropeginterferon alfa-2b-njft effects on fertility have not been assessed [see Use in Specific Populations (8.1, 8.2, 8.3)] .

14 CLINICAL STUDIES

The efficacy and safety of BESREMi were evaluated in the PEGINVERA study, a prospective, multicenter, single-arm trial of 7.5 years duration. The study included 51 adults with polycythemia vera. The mean age at baseline was 56 years (range 35-82 years) with 20 (39%) women and 31 (61%) men. All patients had the JAK2V617F mutation with 16% of subjects being newly diagnosed; 84% had known disease with a median duration of 2.2 years. One-third (33%) of patients were undergoing treatment with hydroxyurea (HU) upon study entry. At baseline, the mean ± SD hematocrit, platelets, and leukocytes were 45% ± 4.0%, 457 ×10^9/L ± 187 ×10^9/L and 11.8 × 10^9/L ± 5.2 × 10^9/L, respectively. Median spleen size was 13.2 cm with 16 (31%) having splenomegaly (defined as a longitudinal diameter of >12 cm for women and >13 cm for men). Eleven patients (22%) had a prior history of a major cardiovascular event including pulmonary embolism (6), stroke (2), myocardial infarction (2) and portal vein thrombosis (1).

In stage I, the maximum tolerated dose, defined as the highest administered dose without dose-limiting toxicities was determined to be 540 mcg. In stage II, an intra-patient dose escalation began at 150 mcg, or 100 mcg if titrating from hydroxyurea, or at the highest dose achieved in those patients enrolled during stage I. Titration with BESREMi occurred every two-weeks at doses of 225 mcg, 300 mcg, 400 mcg and 450 mcg with dose escalation stopping when hematological parameters were stabilized. For patients transitioning from hydroxyurea, the hydroxyurea dose was tapered off over the first 12 weeks of treatment to avoid toxicity. After at least one year on therapy and at a median time of 21.5 months, 28 eligible patients in the PEGINVERA study increased the dosing interval to once every 4 weeks. Because of formulation changes, the recommended starting dose, titration amounts, and maximum dose of BESREMi differ slightly from those used in the trial [see Dosage and Administration (2)] .

The median duration of treatment exposure was 61 months and 53% of patients completed at least 60 months of treatment. Thirty-six patients completed one year of treatment with eleven patients discontinuing after one year of treatment mainly due to treatment emergent adverse events. The mean dose of BESREMi was 237 mcg (± 110) during the treatment period.

The efficacy of BESREMi was evaluated in the PEGINVERA study by assessing complete hematological response (CHR) defined as hematocrit <45% and no phlebotomy in the preceding 2 months, platelets ≤400 × 10^9/L and leukocytes ≤10 × 10^9/L, normal spleen size (longitudinal diameter ≤ 12 cm for females and ≤ 13 cm for males) assessed by ultrasound and absence of thromboembolic events.

The CHR in the treated population during the treatment period was 61% (31/51) (95% CI: 46, 74). The median duration of response was 14.3 months (95% CI: 5.5, 30.1).

Among the patients in the treated population who achieved a CHR, the median time to response was 7.8 months of treatment with BESREMi. It required 1.2 years of treatment with BESREMi for 50% of patients (hydroxyurea-naïve) to achieve a CHR and 1.4 years for 50% of patients with prior hydroxyurea use to achieve a CHR.

A hematological response based only on hematocrit, platelets, and leukocytes was achieved among 80% of patients treated with BESREMi (41/51) (95% CI: 67, 90). The median duration of this response was 20.8 months (95% CI: 13.0, 43.8).

16 HOW SUPPLIED/STORAGE AND HANDLING

16.1 How Supplied

BESREMi (ropeginterferon alfa-2b-njft) injection is a sterile, preservative-free, clear and colorless to slightly yellowish solution for subcutaneous administration in a single-dose prefilled syringe. Each carton contains one 500 mcg/mL prefilled syringe with a 30 gauge, ½ inch safety hypodermic needle (NDC 73536-500-01).

16.2 Storage and Handling

Store in a refrigerator at 36 °F to 46 °F (2 °C to 8 °C) in the original carton to protect from light. Do not freeze.

16.1 How Supplied

BESREMi (ropeginterferon alfa-2b-njft) injection is a sterile, preservative-free, clear and colorless to slightly yellowish solution for subcutaneous administration in a single-dose prefilled syringe. Each carton contains one 500 mcg/mL prefilled syringe with a 30 gauge, ½ inch safety hypodermic needle (NDC 73536-500-01).

16.2 Storage and Handling

Store in a refrigerator at 36 °F to 46 °F (2 °C to 8 °C) in the original carton to protect from light.

Do not freeze.

17 PATIENT COUNSELING INFORMATION

Advise the patient to read the FDA-approved patient labeling (Medication Guide and Instructions for Use).

Depression and Suicide

Inform patients, their caregivers, and family members that suicidal ideation and behavior, as well as new onset or worsening depression have been reported in patients treated with BESREMi. Advise them to be aware of any unusual changes in mood or behavior, new onset or worsening of depression, or the emergence of suicidal thoughts or behavior. Instruct patients, caregivers, and family members to report signs or symptoms of depression to their healthcare provider right away, but to discontinue BESREMi immediately and seek immediate medical attention if suicidal ideation or attempts occur [see Warnings and Precautions (5.1)] .

Endocrine Toxicity

Advise patients to report any signs or symptoms of diabetes or thyroid dysfunction [see Warnings and Precautions (5.2)] .

Cardiovascular Toxicity

Advise patients to report signs or symptoms of cardiovascular toxicity to their healthcare provider [see Warnings and Precautions (5.3)].

Decreased Peripheral Blood Counts

Advise patients to seek prompt medical attention if they experience weakness/fatigue, fever, easy bruising, or frequent nose bleeds [see Warnings and Precautions (5.4)].

Hypersensitivity

Advise patients to seek immediate medical attention if they experience any symptoms of serious hypersensitivity reactions [see Warnings and Precautions (5.5) and Drug Interactions (7)].

Pancreatitis

Advise patients to report signs or symptoms of pancreatitis [see Warnings and Precautions (5.6)] .

Colitis

Advise patients to report signs or symptoms of colitis [see Warnings and Precautions (5.7)] .

Pulmonary Toxicity

Advise patients to report signs or symptoms of pulmonary toxicity [see Warnings and Precautions (5.8)] .

Ophthalmologic Toxicity

Advise patients to report visual changes and to have eye examinations before and during treatment [see Warnings and Precautions (5.9)] .

Hyperlipidemia

Advise patients that BESREMi may increase blood triglycerides and that they will need blood testing to monitor for this toxicity [see Warnings and Precautions (5.10)] .

Hepatotoxicity

Advise patients to report signs or symptoms of hepatic toxicity to their healthcare provider [see Warnings and Precautions (5.11) and Use in Specific Populations (8.7)] .

Renal Toxicity

Advise patients to report signs or symptoms of kidney disease [see Warnings and Precautions (5.12) and Use in Specific Populations (8.6)] .

Dental and Periodontal Toxicity

Advise patients to maintain good oral hygiene and to have regular dental examinations [see Warnings and Precautions (5.13)] .

Dermatologic Toxicity

Advise patients to seek medical attention if significant pruritus, alopecia, rash and/or other dermatological toxicities occur [see Warnings and Precautions (5.14)] .

Hazardous Occupations/Operating Machinery

Advise patients to refrain from engaging in operating heavy or potentially dangerous machinery until they know how BESREMi will affect their abilities. Advise patients who experience dizziness, somnolence and hallucinations not to drive or use heavy machinery [see Warnings and Precautions (5.15)] .

Pregnancy and Contraception

Advise women about the need to use an effective method of contraception while taking BESREMi and for at least 8 weeks after the final dose [see Use in Specific Populations (8.1, 8.3)] .

Lactation

Advise women not to breastfeed during treatment and for 8 weeks after the final dose [see Use in Specific Populations (8.2)] .

Instruction on Injection Technique

Instruct patients on proper storage, preparation and administration techniques for BESREMi. Instruct patients who are self-administering to inject the prescribed dose of BESREMi [see Dosage and Administration (2.4)] .

Manufactured by:
PharmaEssentia Corporation
13F, No. 3, Park Street
Nangang District, Taipei 115,
Taiwan

U.S. License number 2155

Distributed by:
PharmaEssentia USA Corporation
35 Corporate Dr, Suite 325, Burlington, MA 01803, USA

© PharmaEssentia USA Corporation, 2024

Medication Guide
BESREMi® (bez-reh-me)
ropeginterferon alfa-2b-njft
injection, for subcutaneous use

What is the most important information I should know about BESREMi?

BESREMi can cause serious side effects that:

- may cause death, or
- may worsen certain serious diseases that you may already have

Tell your healthcare provider right away if you have any of the symptoms listed below during treatment with BESREMi. If symptoms get worse, or become severe and continue, your healthcare provider may tell you to stop taking BESREMi permanently. These symptoms may go away in some people after they stop taking BESREMi. Mental health problems, including suicide. BESREMi may cause you to develop mood or behavior problems that may get worse during treatment with BESREMi or after your last dose, including:

- irritability (getting upset easily)
- restlessness and agitation
- confusion
- depression (feeling low, feeling bad about yourself or feeling hopeless)
- unusually grand ideas
- acting aggressive
- acting impulsively
- thoughts of hurting yourself or others, or thoughts of suicide

If you develop any of these symptoms, stop using BESREMi right away. You, your caregiver, or family member should call your healthcare provider right away. Your healthcare provider should carefully monitor you during treatment with BESREMi.

New or worsening autoimmune problems. BESREMi may cause autoimmune problems (a condition where the body's immune cells attack other cells or organs in the body), including thyroid problems, increased blood sugar (hyperglycemia), and type I diabetes. In some people who already have an autoimmune problem, it may get worse during your treatment with BESREMi. Tell your healthcare provider if you have any of the following symptoms: tiredness, urinating often, or if you are very thirsty.

Heart problems. BESREMI may cause heart problems, including problems with your heart muscle (cardiomyopathy), heart attack, abnormal heart rhythm (atrial fibrillation), and decreased blood flow to your heart. You should not use BESREMi if you: have high blood pressure that is not controlled, congestive heart failure, a serious abnormal heart rhythm, narrowing of the arteries to your heart, certain types of chest pain (angina), or a recent stroke or heart attack.

If you have a heart problem before you start using BESREMi, your healthcare provider should monitor you closely during treatment with BESREMi.

Call your healthcare provider right away if you get any of the symptoms listed above during treatment with BESREMi. Before and during treatment with BESREMi you will need to see your healthcare provider regularly and have blood tests to monitor your polycythemia vera, and to check for side effects. BESREMi can cause serious side effects. Some of these side effects may cause death. Tell your healthcare provider right away if you have any of the symptoms listed above during treatment with BESREMi. For more information about side effects, see " What are the possible side effects of BESREMi?"

What is BESREMi?

BESREMi is a prescription medicine that is used to treat adults with polycythemia vera.

It is not known if BESREMi is safe and effective in children.

Who should not use BESREMi?

Do not use BESREMi if you:

- have or had severe mental health problems, especially severe depression, thoughts of suicide, or attempted suicide
- have or had a serious or untreated autoimmune disease
- have had a serious allergic reaction to another interferon product or to any of the ingredients in BESREMi. Symptoms of a serious allergic reaction to alpha-interferon may include itching, swelling of your face, tongue, throat, trouble breathing, feeling dizzy or faint, and chest pain. See the end of this Medication Guide for a complete list of ingredients in BESREMi. Ask your healthcare provider if you are not sure.
- have certain types of liver problems
- have received a transplant and take immunosuppressive medicines

Talk to your healthcare provider before taking BESREMi if you have any of these conditions.

Before using BESREMi, tell your healthcare provider about all of your medical conditions, including if you:

- are being treated for a mental illness or had treatment in the past for any mental illness, including depression and have had thoughts of hurting yourself or others.
- have type 1 diabetes
- have or ever had any problems with your heart, including heart attack or high blood pressure
- have or ever had bleeding problems or a blood clot
- have or ever had low blood cell counts
- have a condition that suppresses your immune system, such as certain cancers
- have hepatitis B infection
- have HIV infection
- have kidney problems
- have liver problems
- are pregnant or plan to become pregnant. BESREMi may harm your unborn baby and may cause loss of your pregnancy (miscarriage).
  - Before you start using BESREMi your healthcare provider should do a pregnancy test.
  - You should use effective birth control during treatment and for at least 8 weeks after your final dose of BESREMi. Talk to your healthcare provider about birth control choices for you during treatment with BESREMi.
  - BESREMi can affect your menstrual cycles and may cause your menstrual periods to stop.
  - Tell your healthcare provider if you become pregnant during treatment with BESREMi.
- are breastfeeding or plan to breastfeed. It is not known if BESREMi passes into your breast milk. You should not breastfeed during treatment and for 8 weeks after your final dose of BESREMi.

Tell your healthcare provider about all the medicines you take, including prescription and over-the-counter medicines, vitamins, and herbal supplements.

BESREMi and certain other medicines may affect each other and cause side effects. Know the medicines you take. Keep a list of your medicines and show it to your healthcare provider and pharmacist when you get a new medicine.

How should I use BESREMi?

- See the Instructions for Use that comes with BESREMi for detailed instructions on how to prepare and inject a dose of BESREMi.
- Use BESREMi exactly as your healthcare provider tells you to. Your healthcare provider will tell you how much BESREMi to inject and when to inject it. Do not inject more than your prescribed dose.
- BESREMi is given as an injection under your skin (subcutaneous injection). Your healthcare provider should show you how to prepare and measure your dose of BESREMi, and how to inject yourself before you use BESREMi for the first time.
- You should not inject BESREMi until your healthcare provider has shown you how to use BESREMi the right way. Your healthcare provider will prescribe the amount of BESREMi that is right for you.
- Do not inject more than 1 dose of BESREMi every 2 weeks without talking to your healthcare provider. Do not re-use the single-dose prefilled syringe.
- Your healthcare provider should do blood tests before you start BESREMi, and regularly during treatment to monitor your polycythemia vera, and to check you for side effects.

What should I avoid during treatment with BESREMi?

- BESREMi may cause neurologic symptoms including dizziness, sleepiness, and hallucinations. Avoid driving or using machinery if you develop any of these neurologic symptoms during treatment with BESREMi.

What are the possible side effects of BESREMi?

BESREMi can cause serious side effects including:

- See " What is the most important information I should know about BESREMi?"
- Decreased blood cell counts. Decreased blood cell counts are common with BESREMi and can sometimes also be severe, especially decreased platelets or white blood cells. Your red blood cells may also be decreased. Your healthcare provider should check your blood cell counts before you start and during treatment with BESREMi. If your blood cell counts are low you can develop anemia, infections or have problems with bleeding or bruising.

Call your healthcare provider right away if you develop any of the following symptoms:

- weakness and tiredness
- bruising easily
- you have nose bleeds often
- fever

- chills
- burning and painful urination
- urinating often
- coughing up yellow or pink mucus (phlegm)

- Serious allergic reactions and skin reactions. BESREMi can cause serious, sudden allergic reactions.

Get medical help right away if you get any of the following symptoms:

- skin rash or hives
- itching swelling of your face, eyes, lips tongue, or throat

- trouble breathing
- chest pain
- feeling faint

- Eye problems. BESREMi can cause severe eye problems with your retinas that can lead to vision loss or blindness. You should have an eye exam before and during treatment with BESREMi if you have diabetes or high blood pressure and also have retinal problems. Your healthcare provider may stop BESREMi if you develop new or worse eye problems during treatment with BESREMi.
- Liver problems. BESREMi can cause increases in liver enzymes and liver damage. Your healthcare provider should do blood tests to monitor your liver enzymes and liver function before you start and during treatment with BESREMi.
- Kidney problems. Your healthcare provider will do blood tests to check your kidney function before starting and during treatment with BESREMi. Tell your healthcare provider right away if you develop any symptoms of a kidney problem, including:

- changes in the amount or color of your urine
- blood in your urine

- swelling in your ankles
- loss of appetite

Your healthcare provider may stop BESREMi if you develop severe kidney problems.

- Tooth and gum (periodontal) problems. BESREMi can cause tooth and gum problems which can lead to tooth loss. BESREMi can also cause problems with dry mouth that can damage your teeth and the lining of the mouth during long-term treatment with BESREMi. It is important for you to brush your teeth well, two times each day and have regular dental examinations during treatment with BESREMI.
- Skin problems. BESREMi can cause skin problems. Signs and symptoms of a skin problem with BESREMi include:

- itching
- hair loss
- rash
- redness

- psoriasis
- acne
- thickening of the skin
- excessive sweating

Call your healthcare provider if you develop a rash that is bothersome or covers a large skin area.

The most common side effects of BESREMi include:

- flu like symptoms including: tiredness, weakness, fever, chills, muscle aches, and joint pain
- itching
- sore throat.

These are not all of the possible side effects of BESREMi.

Call your doctor for medical advice about side effects. You may report side effects to FDA at 1-800-FDA-1088.

How should I store BESREMi?

- Store BESREMi in the refrigerator between 36° F to 46° F (2° C to 8° C).
- Keep BESREMi away from heat.
- Do not freeze BESREMi.
- Keep the BESREMi pre-filled syringe in the outer carton to protect it from light.

Keep BESREMi and all medicines out of the reach of children.

General information about the safe and effective use in BESREMi?

Medicines are sometimes prescribed for purposes other than those listed in a Medication Guide. Do not use BESREMi for a condition for which it has not been prescribed. Do not give BESREMi to other people, even if they have the same symptoms that you have. It may harm them. You can ask your pharmacist or healthcare provider for information about BESREMi that is written for health professionals.

What are the ingredients in BESREMi?

Active ingredient: ropeginterferon alfa-2b-njft

Inactive ingredients: benzyl alcohol, glacial acetic acid, polysorbate 80, sodium acetate, sodium chloride, Water for Injection.

Manufactured by: PharmaEssentia Corporation 2F-5 No. 3 YuanQu Street Nangang Dist. Taipei, Taiwan
U.S. License number: 2155
Distributed by: PharmaEssentia USA Corporation, 35 Corporate Dr, Suite 325, Burlington, MA 01803, USA
BESREMi is a trademark/registered trademark of PharmaEssentia
Copyright 2021 PharmaEssentia
For more information, go to www.BESREMi.com or call 1-800-999-2449

This Medication Guide has been approved by the U.S. Food and Drug Administration.

Issued: 11/2021

INSTRUCTIONS FOR USE
BESREMi [bez-reh-me]
(ropeginterferon alfa-2b-njft)
injection, for subcutaneous use
Single-dose prefilled syringe
This "Instructions for Use" contains information on how to prepare and inject BESREMi under your skin (subcutaneous injection) using the single-dose prefilled syringe.
Guide to Prefilled syringe and Needle Parts (Figure A)
Storing BESREMi
Store the BESREMi carton in the refrigerator between 36°F to 46°F (2°C to 8°C) (Figure B).
- Keep your BESREMi prefilled syringes in their original carton (Figure B) while stored.
- Do not freeze the prefilled syringes.
- Do not use a prefilled syringe that has been frozen or left in direct sunlight.
- Keep BESREMi prefilled syringes, needles, and all medicines out of the reach of children.
Important information you need to know before injecting BESREMi
Read this Instructions for Use before using your single-dose BESREMi prefilled syringe for the first time and each time you get a new prescription. There may be new information. This leaflet does not take the place of talking with your healthcare provider about your medical condition or your treatment. Ask your healthcare provider about the right way to prepare and give your BESREMi injection.
- Your healthcare provider will tell you the prescribed dose that you should take and the right amount of BESREMi to measure in the prefilled syringe for your dose. Each time you inject, be sure that you know the prescribed dose of BESREMi to inject. Your dose may change over time.
- BESREMi is for subcutaneous (under the skin) injection only.
- BESREMi is for one-time use only. Do not reuse your prefilled syringe or needle.
- Do not use a prefilled syringe or needle that is damaged or broken. Contact your healthcare provider for a replacement prefilled syringe or additional needles.
- Inject BESREMi into the top of the thighs or lower stomach-area just under the skin. Do not inject BESREMi into any other area of the body.
- Throw away (dispose of) the BESREMi prefilled syringe with needle attached right away after use, even if there is medicine left in the prefilled syringe. See Step 10 in the section " Dispose of used prefilled syringes and needles."
Gather and check supplies
1. | Prepare BESREMi Prefilled Syringe
 | 1.1. | Take the BESREMi carton out of the refrigerator (Figure E).
 | 1.2. | Check the expiration date ("EXP") on the top panel of the carton to make sure it has not passed (Figure F). Do not use the prefilled syringe if the expiration date has passed.
 | 1.3. | Let carton containing the BESREMi prefilled syringe sit on a clean work surface for 15 to 30 minutes to allow it to come to room temperature (Figure G). Do not warm the prefilled syringe any other way.
2. | Gather supplies for injection
 | 2.1. | After allowing the prefilled syringe to come to room temperature for 15 to 30 minutes inside the carton, gather the following additional supplies. Alcohol Swab (Figure H).; FDA-cleared Sharps Disposal Container (Figure I); A paper towel, sink, or trash can to minimize mess during dose adjustment (Figure J).; Optional Items: Gauze or Cotton Ball and a Small Adhesive Bandage (Figure K).
3. | Wash hands and remove syringe from tray
 | 3.1. | Wash your hands with soap and water, then dry your hands (Figure L).
 | 3.2. | Open the carton and remove the clear plastic tray that holds the BESREMi prefilled syringe and needle package (Figure M).
 | 3.3. | Remove the needle package and BESREMi prefilled syringe from the plastic tray. Hold the prefilled syringe by the middle of the syringe body during removal (Figure N).
4. | Check the liquid medicine in the BESREMi prefilled syringe
 | 4.1. | Check the liquid medicine in the prefilled syringe (Figure O). The liquid should be clear and colorless to slightly yellow, and should not have particles. Do not use the prefilled syringe if the liquid is cloudy, discolored, or contains particles. Contact your healthcare provider or pharmacist.
 | 4.2. | Check the syringe to see if it is damaged or broken (Figure O). Do not use if it shows any signs of damage or breakage. Contact your healthcare provider or pharmacist.
Prepare syringe for injection
5. | Attach the needle to the BESREMi prefilled syringe
 | 5.1. | Carefully open the needle package, remove the needle, and set it aside (Figure P). Throw away the packaging into household trash.
 | 5.2. | Hold the prefilled syringe as shown. Remove the prefilled syringe cap by unscrewing it counter-clockwise (Figure Q). Throw away the syringe cap into household trash. Do not allow the tip of the prefilled syringe to touch anything.
 | 5.3. | Attach the needle to the prefilled syringe by firmly pushing it into the collar of the syringe and then screwing (turn clock-wise) it on until it feels securely attached (Figure R).; The needle should now be assembled to the prefilled syringe (Figure S).
6. | Choose and clean injection site
 | 6.1. | Choose one of the following injection sites (Figure T):; - Lower stomach (abdomen) area, at least 2 inches away from the belly button, - Top of thighs. Do not inject into skin that is irritated, red, bruised, infected, or scarred. BESREMi is for subcutaneous (under the skin) injection only. Rotate (change) the injection site for each injection.
 | 6.2. | Clean the chosen injection site with an alcohol swab and let it air dry (Figure U). Do not blow on or touch the injection site after it has been cleaned.
7. | Uncap needle and move air bubbles to top
 | 7.1. | Pull the pink needle shield back (Figure V). Note: The pink needle shield will be used after the injection to cover the needle and protect you from needle-stick injuries.
 | 7.2. | Hold the syringe from the syringe body. Remove the clear needle cap by pulling it straight off (Figure W). Throw away the needle cap into household trash. Do not recap needle.
 | 7.3. | Hold the prefilled syringe with the needle pointing up. Tap on the body of the prefilled syringe to move any air bubbles to the top (Figure X).
8. | Set your dose
 | 8.1. | Check your prescription to identify your prescribed dose (Figure Y). Depending on your prescribed dose, you may have to adjust the dose in the syringe by getting rid of (discarding) some medicine from the prefilled syringe before you inject the medicine.
 | 8.2. | To set your dose follow the 4 steps below:; 1. Hold the prefilled syringe at eye level with the needle pointing straight up over a paper towel, sink, or trash can. 2. Check that you can see the dose lines and number markings on the prefilled syringe. 3. Pinch the end of the plunger as shown (Figure Z). 4. Slowly push up on the plunger to remove liquid medicine until the top edge of the gray stopper lines up with the marking for your prescribed dose (Figure Z). Keep holding straight up as you set the dose. Important: If you accidentally remove too much liquid medicine, do not inject. Contact your healthcare provider or pharmacist.
Inject BESREMi
9. | Give Injection
 | 9.1. | Pinch the chosen injection site (Figure AA).
 | 9.2. | While pinching the skin, insert the needle at a 45 to 90 degree angle into the pinched skin (Figure AB). Then release the pinched skin.
 | 9.3. | Inject the medicine by slowly pressing down on the plunger all the way until it stops (Figure AC).
 | 9.4. | After all the liquid medicine is injected, remove the needle from the skin (Figure AD).
 | 9.5 | Cover needle Carefully push the pink needle shield over the needle until it snaps into place and covers the needle (Figure AE). This helps prevent needle-stick injuries. Do not recap the needle using the needle cap. Only use the pink needle shield to cover the needle.
Do not reuse the prefilled syringe and needle.
Disposing of used prefilled syringes and needles
10. | Dispose of used prefilled syringes and needles.; - Put your used prefilled syringes and needles in a FDA-cleared sharps disposal container right away after use (Figure AF). Do not throw away (dispose of) loose prefilled syringes and needles in the household trash. - If you do not have a FDA-cleared sharps disposal container, you may use a household container that is: - made of a heavy-duty plastic, - can be closed with a tight-fitting, puncture-resistant lid without sharps being able to come out, - upright and stable during use, - leak-resistant, and - properly labeled to warn of hazardous waste inside the container. - When your sharps disposal container is almost full, you will need to follow your community guidelines for the right way to dispose of your sharps disposal container. There may be state or local laws about how you should throw away used needles and syringes. For more information about safe sharps disposal, and for specific information about sharps disposal in the state that you live in, go to the FDA's website at: http://www.fda.gov/safesharpsdisposal. - Do not dispose of your sharps disposal container in your household trash unless your community guidelines permit this. Do not recycle your used sharps disposal container. - Always keep the sharps disposal container out of the reach of children.
11 | Check injection site.
 | 11.1 | If there is a small amount of blood or liquid at the injection site, press a gauze or cotton ball over the injection site until the bleeding stops (Figure AG).
 | 11.2 | Do not rub the injection site. If needed, you may apply a small adhesive bandage.
Additional information.
For additional information about BESREMi and a video demonstration on how to use BESREMi, go to:
www.BESREMi.com
Manufactured by:
PharmaEssentia Corporation
2F-5 No. 3 YuanQu Street
Nangang Dist. Taipei, Taiwan
U.S. License number: 2155
Distributed by:
PharmaEssentia Corporation
35 Corporate Drive, Suite 325, Burlington, MA 01803, USA
BESREMi is a trademark/registered trademark of PharmaEssentia
Copyright 2021 PharmaEssentia
This "Instructions for Use" has been approved by the U.S. Food and Drug Administration. |  |  | Issued: November 2021

PRINCIPAL DISPLAY PANEL - 500 mcg/mL Syringe Label

BESREMi®
(ropeginterferon alfa-2b-njft)
INJECTION

500 mcg/mL
For Subcutaneous Use

LOT:
EXP:

Rx Only
PharmaEssentia Corp.

PRINCIPAL DISPLAY PANEL - 500 mcg/mL Syringe Carton

BESREMi®
(ropeginterferon alfa-2b-njft)
INJECTION

500 mcg/mL
For Subcutaneous Use. Rx Only

One Single-Dose Prefilled Syringe

CAUTION: Prefilled syringe contains more medication than your
prescribed dose.

ATTENTION: Dispense the Enclosed Medication Guide to Each Patient.

NDC 73536-500-01

Contains:

- One Single-Dose
  Prefilled Syringe
- One Injection
  Needle
- Full Prescribing
  Information
- Instructions for Use
- Medication Guide

PharmaEssentia™